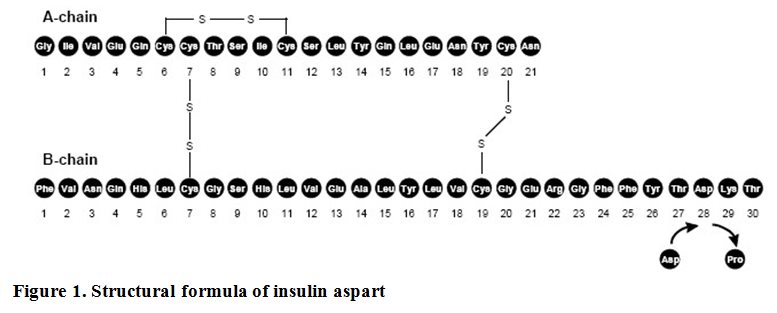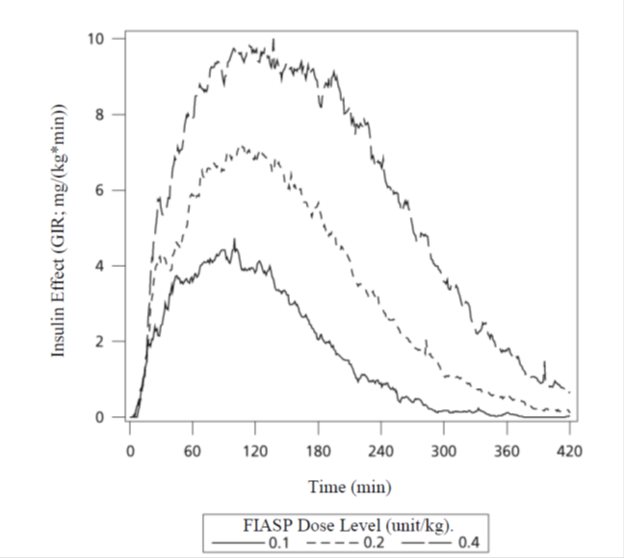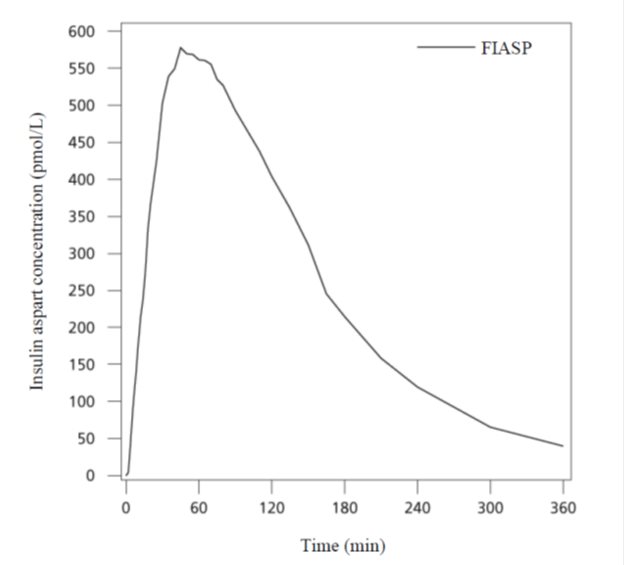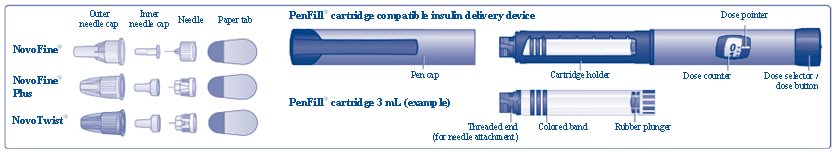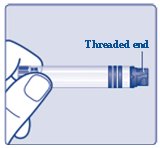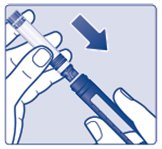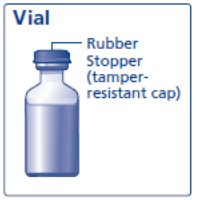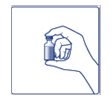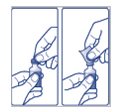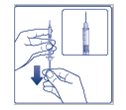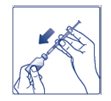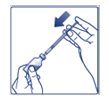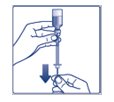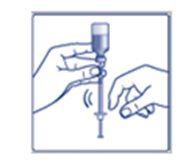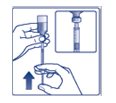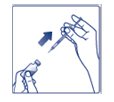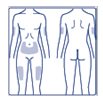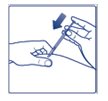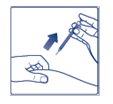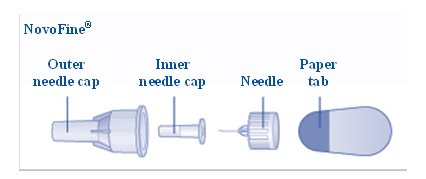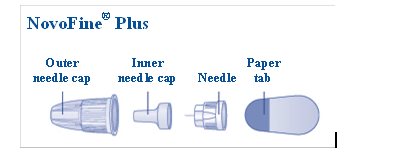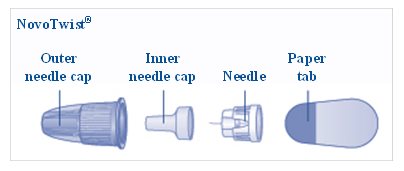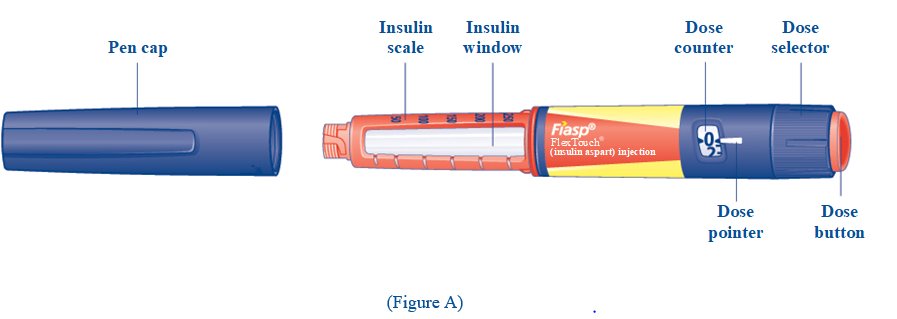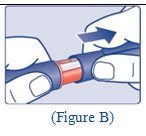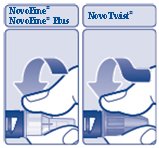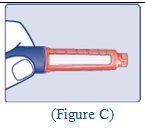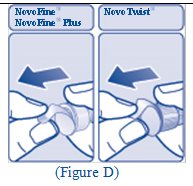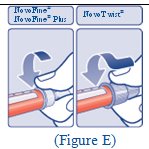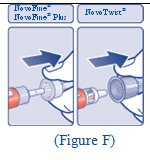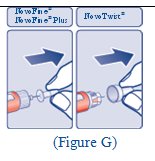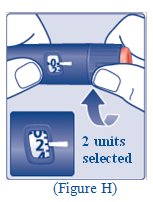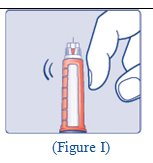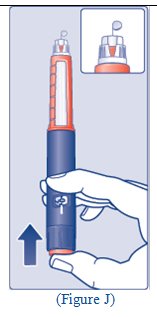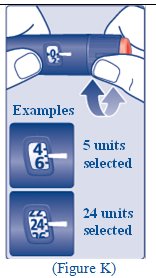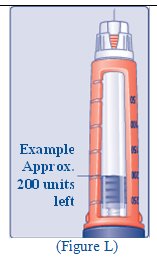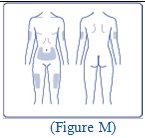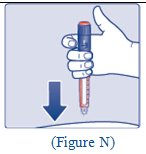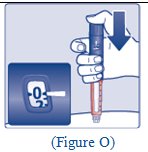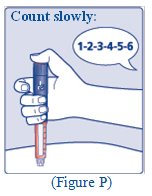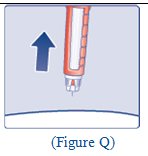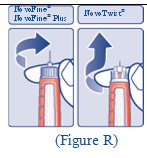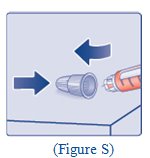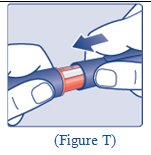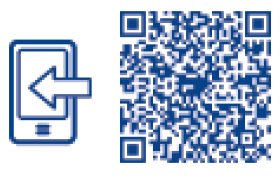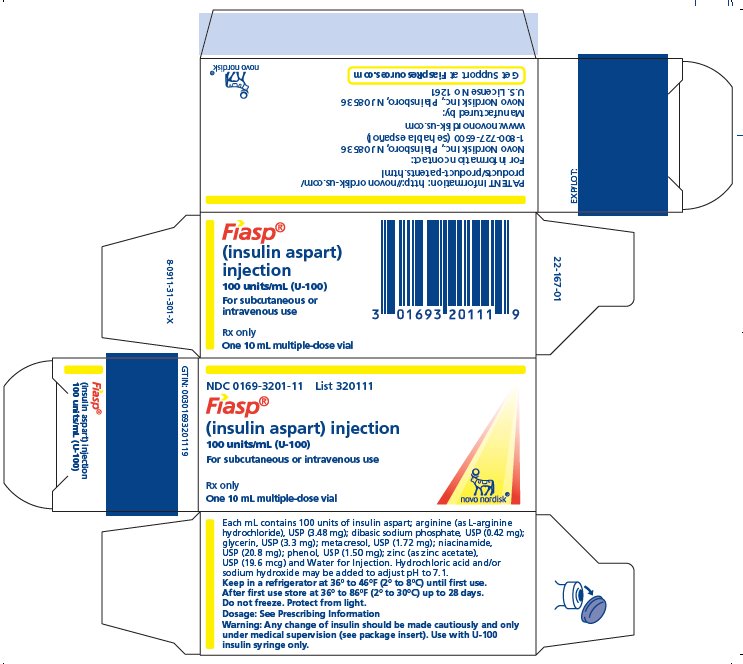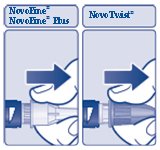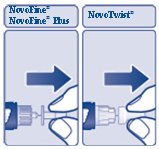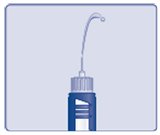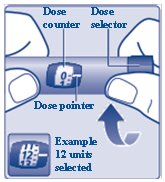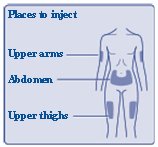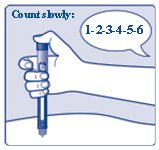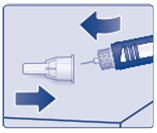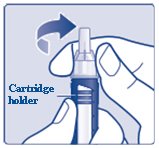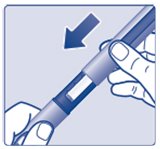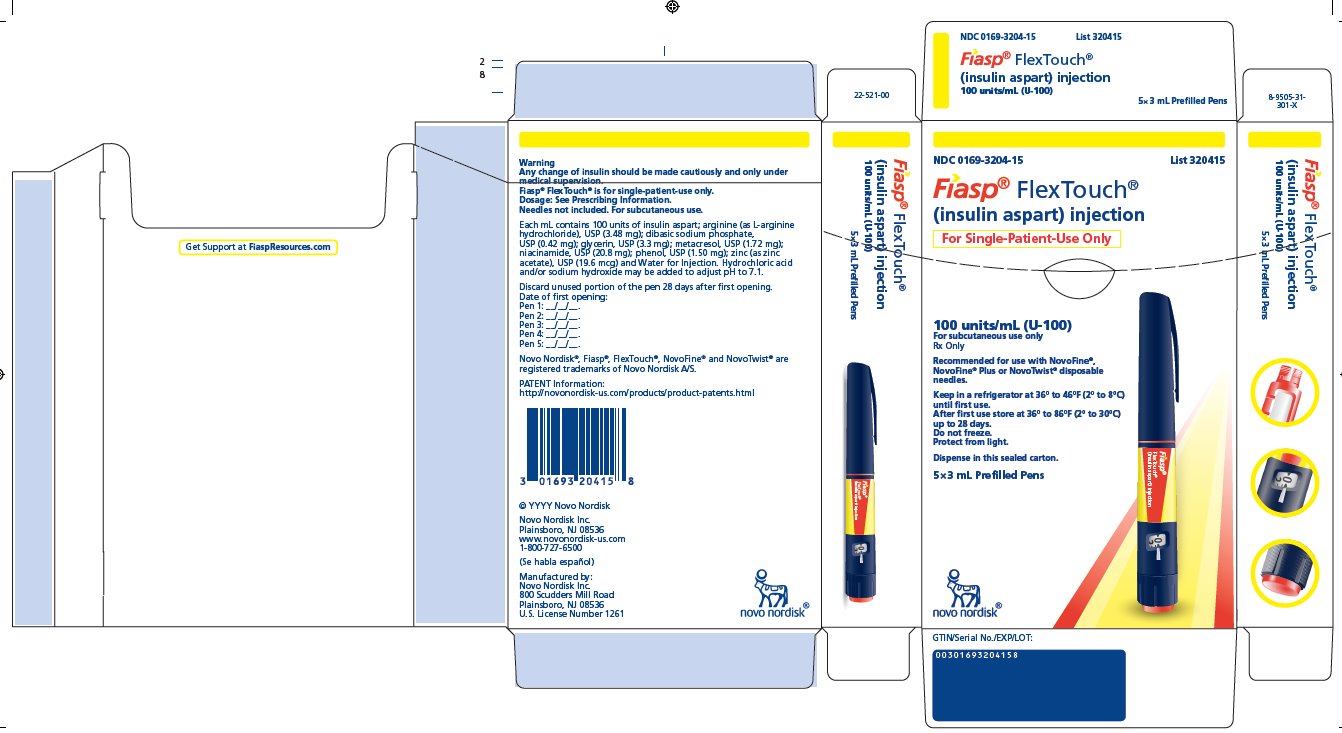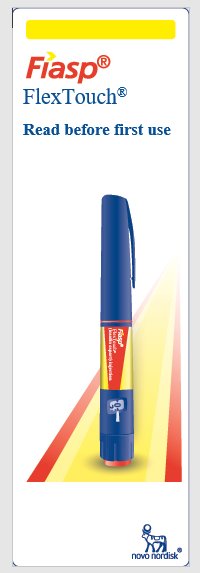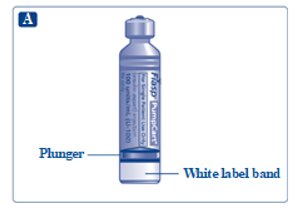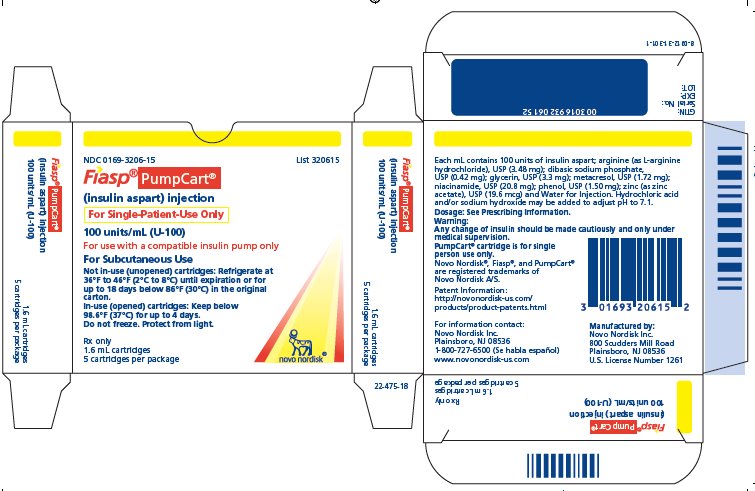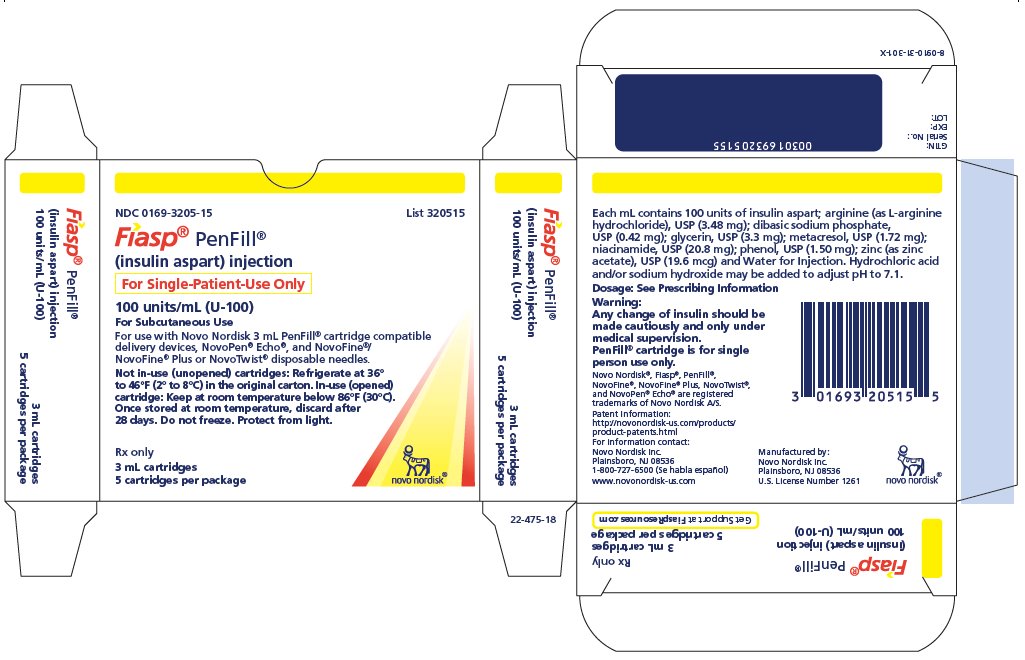 DRUG LABEL: Fiasp
NDC: 0169-3201 | Form: INJECTION, SOLUTION
Manufacturer: Novo Nordisk
Category: prescription | Type: HUMAN PRESCRIPTION DRUG LABEL
Date: 20230621

ACTIVE INGREDIENTS: INSULIN ASPART 100 [iU]/1 mL
INACTIVE INGREDIENTS: WATER

HIGHLIGHTS OF PRESCRIBING INFORMATION

These highlights do not include all the information needed to use FIASP safely and effectively. See full prescribing information for FIASP.
FIASP® (insulin aspart) injection, for subcutaneous or intravenous use
Initial U.S. Approval: 2000

1 INDICATIONS AND USAGE

- FIASP is a rapid-acting human insulin analog indicated to improve glycemic control in adult and pediatric patients with diabetes mellitus (1).

2 DOSAGE AND ADMINISTRATION

- Individualize and adjust the dosage of FIASP based on route of administration, individual’s metabolic needs, blood glucose monitoring results and glycemic control goal (2.3).
- Dosage adjustments may be needed when switching from another insulin, with changes in physical activity, changes in concomitant medications, changes in meal patterns, changes in renal or hepatic function or during acute illness (2.3).
- Subcutaneous injection (2.2):
  - Inject at the start of a meal or within 20 minutes after starting a meal into the abdomen, upper arm, or thigh.
  - Rotate injection sites within the same region to reduce the risk of lipodystrophy and localized cutaneous amyloidosis.
  - Should generally be used in regimens with an intermediate- or long-acting insulin.
- Continuous Subcutaneous Infusion (Insulin Pump) (2.2):
  - Refer to the insulin infusion pump user manual to see if FIASP can be used. Use in accordance with the insulin pumps’ instructions for use.
  - Administer by continuous subcutaneous infusion using an insulin pump in a region recommended in the instructions from the pump manufacturer. Rotate infusion sites within the same region to reduce the risk of lipodystrophy and localized cutaneous amyloidosis.
- Intravenous Infusion: Administer only under medical supervision after diluting to concentrations from 0.5 to 1 unit/mL insulin aspart in infusion systems using polypropylene infusion bags (2.2).

3 DOSAGE FORMS AND STRENGTHS

Injection: 100 units/mL (U-100) available as:

- 10 mL multiple-dose vial (3)
- 3 mL single-patient-use FIASP FlexTouch® pen (3)
- 3 mL single-patient-use PenFill® cartridges for use in a PenFill cartridge device (3)
- 1.6 mL single-patient-use PumpCart® cartridges for use in a compatible insulin pump (3)

4 CONTRAINDICATIONS

- During episodes of hypoglycemia (4).
- Hypersensitivity to insulin aspart or any of the excipients in FIASP (4).

5 WARNINGS AND PRECAUTIONS

- Never share a FIASP FlexTouch pen, PenFill cartridge or PenFill cartridge device between patients, even if the needle is changed (5.1).
- Hyperglycemia or hypoglycemia with changes in insulin regimen: Make changes to a patient’s insulin regimen (e.g., insulin strength, manufacturer, type, injection site or method of administration) under close medical supervision with increased frequency of blood glucose monitoring (5.2).
- Hypoglycemia: May be life-threatening. Increase frequency of glucose monitoring with changes to: insulin dosage, co-administered glucose lowering medications, meal pattern, physical activity; and in patients with renal impairment or hepatic impairment or hypoglycemia unawareness (5.3).
- Hypoglycemia due to medication errors: Accidental mix-ups between insulin products can occur. Instruct patients to check insulin labels before injection (5.4).
- Hypokalemia: May be life-threatening. Monitor potassium levels in patients at risk for hypokalemia and treat if indicated (5.5).
- Hypersensitivity reactions: Severe, life-threatening, generalized allergy, including anaphylaxis, can occur. Discontinue FIASP, monitor and treat if indicated (5.6).
- Fluid retention and heart failure with concomitant use of thiazolidinediones (TZDs): Observe for signs and symptoms of heart failure; consider dosage reduction or discontinuation if heart failure occurs (5.7).
- Hyperglycemia and Ketoacidosis Due to Insulin Pump Device Malfunction: Monitor glucose and administer FIASP by subcutaneous injection if pump malfunction occurs (5.8).

6 ADVERSE REACTIONS

Adverse reactions observed with FIASP include: hypoglycemia, allergic reactions, hypersensitivity, injection/infusion site reactions, lipodystrophy, and weight gain (6.1).

To report SUSPECTED ADVERSE REACTIONS, contact Novo Nordisk Inc. at 1-800-727-6500 or FDA at 1-800-FDA-1088 or www.fda.gov/medwatch.

7 DRUG INTERACTIONS

- Drugs that Increase Hypoglycemia Risk or Increase or Decrease Blood Glucose Lowering Effect: Adjustment of dosage may be needed; closely monitor blood glucose (7).
- Drugs that Blunt Hypoglycemia Signs and Symptoms (e.g., beta-blockers, clonidine, guanethidine, and reserpine): Increased frequency of glucose monitoring may be required (7).

FULL PRESCRIBING INFORMATION

1 INDICATIONS AND USAGE

FIASP is indicated to improve glycemic control in adult and pediatric patients with diabetes mellitus.

2 DOSAGE AND ADMINISTRATION

2.1 Important Preparation and Administration Instructions

- Always check insulin label before administration [see Warnings and Precautions (5.4)].
- Inspect FIASP visually before use. It should appear clear and colorless. Do not use FIASP if particulate matter or coloration is seen.
- Use FIASP FlexTouch pen with caution in patients with visual impairment who may rely on audible clicks to dial their dose.
- Use PenFill cartridges with caution in patients with visual impairment.
- Do not mix FIASP with any other insulin.

2.2 Route of Administration Instructions

Subcutaneous Injection:

- Inject FIASP at the start of a meal or within 20 minutes after starting a meal subcutaneously into the abdomen, upper arm, or thigh.
- Rotate injection sites within the same region from one injection to the next to reduce the risk of lipodystrophy and localized cutaneous amyloidosis. Do not inject into areas of lipodystrophy or localized cutaneous amyloidosis [see Adverse Reactions (6.1, 6.2)].
- FIASP given by subcutaneous injection should generally be used in regimens with intermediate or long-acting insulin.
- Instruct patients on basal-bolus treatment who forget a mealtime dose to monitor their blood glucose level to decide if an insulin dose is needed, and to resume their usual dosing schedule at the next meal.
- The FIASP FlexTouch pen dials in 1 unit increments.

Continuous Subcutaneous Infusion (Insulin Pump):

- Refer to the continuous subcutaneous insulin infusion pump user manual to see if FIASP or FIASP PumpCart can be used with the insulin pump. Use FIASP and FIASP PumpCart in accordance with the insulin pump system’s instructions for use.
- Administer FIASP by continuous subcutaneous infusion in a region recommended in the instructions from the pump manufacturer. Rotate infusion sites within the same region to reduce the risk of lipodystrophy and localized cutaneous amyloidosis. Do not infuse into areas of lipodystrophy or localized cutaneous amyloidosis [see Warnings and Precautions (5.2) Adverse Reactions (6.1)].
- Train patients using continuous subcutaneous insulin infusion therapy to administer insulin by injection and have alternate insulin therapy available in case of insulin pump failure [see Warnings and Precautions (5.8)].
- Change FIASP in the pump reservoir at least every 6 days or replace the PumpCart cartridge at least every 4 days, or according to the pump user manual, whichever is shorter. Follow the FIASP-specific information for in-use time because FIASP-specific information may differ from general insulin pump user manual instructions.
- Change the infusion sets and the infusion set insertion site according to the manufacturers user manual.
- Do not mix with other insulins or diluents in the insulin pump.
- Do not expose FIASP in the pump reservoir to temperatures greater than 37°C (98.6°F).

Intravenous Administration:

- Administer FIASP intravenously only under medical supervision with close monitoring of blood glucose and potassium levels to avoid hypoglycemia and hypokalemia [see Warnings and Precautions (5.3, 5.5)].
- Dilute FIASP to concentrations from 0.5 unit/mL to 1 unit/mL insulin aspart in infusion systems using polypropylene infusion bags.
- FIASP is stable at room temperature at 20°C to 25°C (68°F to 77°F) for 24 hours in 0.9% sodium chloride or 5% dextrose infusion fluids.

2.3 Dosage Recommendations

- Individualize the dosage of FIASP based on the route of administration, patient’s metabolic needs, blood glucose monitoring results, and glycemic control goal.
- If converting from another mealtime insulin to FIASP, the initial change can be done on a unit-to-unit basis.
- Dose adjustments may be needed when switching from another insulin, with changes in physical activity, changes in concomitant medications, changes in meal patterns (i.e., macronutrient content or timing of food intake), changes in renal or hepatic function or during acute illness to minimize the risk of hypoglycemia or hyperglycemia [see Warnings and Precautions (5.2, 5.3) and Drug Interactions (7), and Use in Specific Populations (8.6, 8.7)].
- Closely monitor blood glucose when converting insulins used in insulin pumps as individualization of insulin pump parameters may be necessary to minimize the risk of hypoglycemia and hyperglycemia [see Warnings and Precautions (5.2, 5.3) and Adverse Reactions (6.1)]
- During changes to a patient’s insulin regimen, increase the frequency of blood glucose monitoring [see Warnings and Precautions (5.2)].
- Dosage adjustment may be needed when FIASP is co-administered with certain drugs [see Drug Interactions (7)].

3 DOSAGE FORMS AND STRENGTHS

Injection: 100 units of insulin aspart per mL (U-100) is available as a clear and colorless solution in:

- 10 mL multiple-dose vial
- 3 mL single-patient-use FIASP FlexTouch pen
- 3 mL single-patient-use PenFill cartridges for use in a PenFill cartridge delivery device
- 1.6 mL single-patient-use PumpCart cartridges for use in a compatible insulin pump.

4 CONTRAINDICATIONS

FIASP is contraindicated:

- During episodes of hypoglycemia [see Warnings and Precautions (5.3)].
- In patients with known hypersensitivity to insulin aspart or any of the excipients in FIASP [see Warnings and Precautions (5.6)].

5 WARNINGS AND PRECAUTIONS

5.1 Never Share a FIASP FlexTouch Pen, PenFill Cartridge or PenFill Cartridge Device Between Patients

FIASP FlexTouch disposable pen, PenFill cartridge and PenFill cartridge devices should never be shared between patients, even if the needle is changed. Patients using FIASP vials should never share needles or syringes with another person. Sharing poses a risk for transmission of blood-borne pathogens.

5.2 Hyperglycemia or Hypoglycemia with Changes in Insulin Regimen

Changes in an insulin regimen (e.g., insulin strength, manufacturer, type, injection site or method of administration) may affect glycemic control and predispose to hypoglycemia [see Warnings and Precautions (5.3)] or hyperglycemia. Repeated insulin injections into areas of lipodystrophy or localized cutaneous amyloidosis have been reported to result in hyperglycemia; and a sudden change in the injection site (to an unaffected area) has been reported to result in hypoglycemia [see Adverse Reactions (6.1, 6.2)].

Make any changes to a patient’s insulin regimen under close medical supervision with increased frequency of blood glucose monitoring. Advise patients who have repeatedly injected into areas of lipodystrophy or localized cutaneous amyloidosis to change the injection site to unaffected areas and closely monitor for hypoglycemia. For patients with type 2 diabetes mellitus, dosage adjustments in concomitant anti-diabetic treatment may be needed.

5.3 Hypoglycemia

Hypoglycemia is the most common adverse reaction of all insulin therapies, including FIASP [see Adverse Reactions (6.1)]. Severe hypoglycemia can cause seizures, may lead to unconsciousness, may be life-threatening, or cause death. Hypoglycemia can impair concentration ability and reaction time; this may place an individual and others at risk in situations where these abilities are important (e.g., driving or operating other machinery). FIASP, or any insulin, should not be used during episodes of hypoglycemia [see Contraindications (4)].

Hypoglycemia can happen suddenly and symptoms may differ in each individual and change over time in the same individual. Symptomatic awareness of hypoglycemia may be less pronounced in patients with longstanding diabetes, in patients with diabetic nerve disease, in patients using medications that block the sympathetic nervous system (e.g., beta-blockers) [see Drug Interactions (7)], or in patients who experience recurrent hypoglycemia.

Risk Factors for Hypoglycemia

The risk of hypoglycemia after an injection is related to the duration of action of the insulin and, in general, is highest when the glucose lowering effect of the insulin is maximal. The timing of hypoglycemia usually reflects the time-action profile of the administered insulin formulation. As with all insulin preparations, the glucose lowering effect time course of FIASP may vary in different individuals or at different times in the same individual and depends on many conditions, including the area of injection as well as the injection site blood supply and temperature [see Use in Specific Populations (8.4), Clinical Pharmacology (12.2)].

Other factors which may increase the risk of hypoglycemia include changes in meal pattern (e.g., macronutrient content or timing of meals), changes in level of physical activity, or changes to co-administered medication [see Drug Interactions (7)]. Patients with renal or hepatic impairment may be at higher risk of hypoglycemia [see Use in Specific Populations (8.6, 8.7)].

Risk Mitigation Strategies for Hypoglycemia

Patients and caregivers must be educated to recognize and manage hypoglycemia. Self-monitoring of blood glucose plays an essential role in the prevention and management of hypoglycemia. In patients at higher risk for hypoglycemia and patients who have reduced symptomatic awareness of hypoglycemia, increased frequency of blood glucose monitoring is recommended.

5.4 Hypoglycemia Due to Medication Errors

Accidental mix-ups between insulin products have been reported. To avoid medication errors between FIASP and other insulins, instruct patients to always check the insulin label before each injection.

5.5 Hypokalemia

All insulin products, including FIASP, can cause a shift in potassium from the extracellular to intracellular space, possibly leading to hypokalemia. Untreated hypokalemia may cause respiratory paralysis, ventricular arrhythmia and death. Monitor potassium levels in patients at risk for hypokalemia if indicated (e.g., patients using potassium-lowering medications, patients taking medications sensitive to potassium concentrations).

5.6 Hypersensitivity and Allergic Reactions

Severe, life-threatening, generalized allergy, including anaphylaxis, can occur with insulin products, including FIASP [see Adverse Reactions (6.1)]. If hypersensitivity reactions occur, discontinue FIASP; treat per standard of care and monitor until symptoms and signs resolve. FIASP is contraindicated in patients who have had hypersensitivity reactions to insulin aspart, or any of the excipients in FIASP [see Contraindications (4)].

5.7 Fluid Retention and Heart Failure with Concomitant Use of PPAR-Gamma Agonists

Thiazolidinediones (TZDs), which are peroxisome proliferator-activated receptor (PPAR)-gamma agonists, can cause dose-related fluid retention, particularly when used in combination with insulin. Fluid retention may lead to or exacerbate heart failure. Patients treated with insulin, including FIASP, and a PPAR-gamma agonist should be observed for signs and symptoms of heart failure. If heart failure develops, it should be managed according to current standards of care, and discontinuation or dose reduction of the PPAR-gamma agonist must be considered.

5.8 Hyperglycemia and Ketoacidosis Due to Insulin Pump Device Malfunction

Pump or infusion set malfunctions can lead to a rapid onset of hyperglycemia and ketoacidosis. Prompt identification and correction of the cause of hyperglycemia or ketosis is necessary. Interim therapy with subcutaneous injection of FIASP may be required. Patients using continuous subcutaneous insulin infusion pump therapy must be trained to administer insulin by injection and have alternate insulin therapy available in case of pump failure [see Dosage and Administration (2.2), How Supplied/Storage and Handling (16.2), and Patient Counseling Information (17)].

6 ADVERSE REACTIONS

The following clinically significant adverse reactions are described elsewhere in labeling:

- Hyperglycemia or Hypoglycemia with Changes in Insulin Regimen [see Warnings and Precautions (5.2)]
- Hypoglycemia [see Warnings and Precautions (5.3)]
- Hypokalemia [see Warnings and Precautions (5.5)]
- Hypersensitivity and allergic reactions [see Warnings and Precautions (5.6)]

6.1 Clinical Trial Experience

Because clinical trials are conducted under widely varying conditions, adverse reaction rates observed in the clinical trials of a drug cannot be directly compared to rates in the clinical trials of another drug, and may not reflect the rates actually observed in clinical practice.

The data in Table 1 reflect the exposure of 763 adult patients with type 1 diabetes mellitus to FIASP in one clinical trial with a mean exposure duration of 25 weeks [see Clinical Studies (14.2)]. The mean age was 44.4 years and the mean duration of diabetes was 19.9 years. 59% were male, 93% were White, and 2% were Black or African American; and 7% were Hispanic or Latino. The mean BMI was 26.7 kg/m^2 and the mean HbA1c at baseline was 7.6%.

The data in Table 2 reflect the exposure of 341 adult patients with type 2 diabetes mellitus to FIASP in one clinical trial with a mean exposure duration of 24 weeks [see Clinical Studies (14)]. The mean age was 59.6 years and the mean duration of diabetes was 13.2 years. 47% were male, 80% were White, and 6% were Black or African American; and 8% were Hispanic or Latino. The mean BMI was 31.5 kg/m^2 and the mean HbA1c at baseline was 8.0%.

The data in Table 3 reflect the exposure of 519 pediatric patients with type 1 diabetes mellitus to FIASP in one clinical trial with a mean exposure duration of 26 weeks [see Clinical Studies (14.3)]. The mean age was 11.7 years and the mean duration of diabetes mellitus was 4.4 years. 54% were male, 81% were White, 16% were Asian and 2% were Black or African American. The mean BMI was 19.7 kg/m^2 and the mean HbA1c at baseline was 7.6%.

Common adverse reactions, excluding hypoglycemia, were defined as events occurring in ≥5% and occurring at the same rate or greater for FIASP-treated patients than comparator-treated patients.

Table 1. Adverse Reactions (%*) in Adult Patients with Type 1 Diabetes Mellitus

 | Mealtime FIASP + Insulin detemir (N=386) | Postmeal FIASP + Insulin detemir (N=377)
Nasopharyngitis | 20.2 | 23.9
Upper respiratory tract infection | 9.1 | 7.4
Nausea | 4.9 | 5.0
Diarrhea | 5.4 | 3.2
Back pain | 5.2 | 4.0

*Incidence ≥ 5% and occurring at the same rate or greater with FIASP than comparator

Table 2. Adverse Reactions (%*) in Adult Patients with Type 2 Diabetes Mellitus

 | FIASP + Insulin glargine (N=341)
Urinary tract infection | 5.9

*Incidence ≥ 5% and occurring at the same rate or greater with FIASP than comparator

Table 3: Adverse Reactions (%*) in Pediatric Patients with Type 1 Diabetes Mellitus

 | Mealtime FIASP + Insulin degludec; (N=261) | Postmeal FIASP + Insulin degludec; (N=258)
Viral upper respiratory tract infection; Upper respiratory tract infection; Influenza; Rhinitis; Headache; Pyrexia; Vomiting | 23.0; 8.4; 7.7; 3.8; 6.1; 8.4; 3.4 | 20.5; 12.4; 5.8; 6.2; 10.1; 6.2; 8.1

*Incidence ≥ 5% and occurring at the same rate or greater with FIASP than comparator

Hypoglycemia

Hypoglycemia is the most commonly observed adverse reaction in patients using insulin, including FIASP. The rates of reported hypoglycemia depend on the definition of hypoglycemia used, diabetes type, insulin dose, intensity of glucose control, background therapies, and other intrinsic and extrinsic patient factors. For these reasons, comparing rates of hypoglycemia in clinical trials for FIASP with the incidence of hypoglycemia for other products may be misleading and also, may not be representative of hypoglycemia rates that occur in clinical practice.

Incidence rates for severe hypoglycemia in adults with type 1 and type 2 diabetes mellitus and pediatric patients with type 1 diabetes mellitus treated with FIASP in clinical trials are shown in Table 4 [see Clinical Studies (14)].

Table 4. Proportion (%) of Patients with Type 1 Diabetes and Type 2 Diabetes Mellitus Experiencing at Least One Episode of Severe Hypoglycemia in Adult and Pediatric Clinical Trials

 | Study A (Type 1); Adults |  | Study B (Type 2); Adults | Study E (Type 1); Pediatric |  | Study D; (Type 1 CSII)
 | Mealtime FIASP + Insulin detemir; (N=386) | Postmeal FIASP + Insulin detemir; (N=377) | FIASP + Insulin glargine; (N=341) | Mealtime FIASP + Insulin degludec; (N=261) | Postmeal FIASP + Insulin degludec; (N=258) | FIASP; (N=236)
Severe hypoglycemia* | 6.7 | 8.0 | 3.2 | 1.1 | 3.1 | 4.7

*Severe hypoglycemia: an episode requiring assistance of another person to actively administer carbohydrate, glucagon, or other resuscitative actions

Blood glucose confirmed hypoglycemia was defined as a self-measured glucose calibrated to plasma of less than 56 mg/dL.

In Study D, adult patients with type 1 diabetes mellitus treated with FIASP in a pump reported a higher rate of blood glucose confirmed hypoglycemic episodes within the first hour after a meal compared to patients treated with NovoLog [see Clinical Trials (14.5)].

In Study E, pediatric patients with type 1 diabetes mellitus treated with mealtime and postmeal FIASP reported a higher rate of blood glucose confirmed hypoglycemic episodes compared to patients treated with NovoLog; the imbalance was greater during the nocturnal period [see Use in Specific Populations (8.4), Clinical Trials (14.3)].

Allergic Reactions

Severe, life-threatening, generalized allergy, including anaphylaxis, generalized skin reactions, angioedema, bronchospasm, hypotension, and shock may occur with any insulin, including FIASP, and may be life threatening. In the clinical program, generalized hypersensitivity reactions (manifested by generalized skin rash and facial edema) were reported in 0.4% of adult patients treated with FIASP. Allergic skin manifestations reported with FIASP in 1.7% of adult patients from the clinical program include eczema, rash, rash pruritic, urticaria and dermatitis. In Study D, allergic reactions were reported in 4.2% of adult patients with type 1 diabetes mellitus treated with FIASP. In Study E, allergic reactions were reported in 4% of pediatric patients with type 1 diabetes mellitus treated with FIASP.

Lipodystrophy

Administration of insulin, including FIASP, has resulted in lipohypertrophy (enlargement or thickening of tissue) and lipoatrophy (depression in the skin). In the clinical program, lipodystrophy was reported in 0.4% of adult patients and 2.1% of pediatric patients treated with FIASP [see Dosage and Administration (2.2)].

Injection/Infusion Site Reactions

As with other insulin therapy, patients may experience rash, redness, inflammation, pain, bruising or itching at the site of FIASP injection or infusion. These reactions usually resolve in a few days to a few weeks, but in some occasions, may require discontinuation of FIASP. In the clinical program, injection site reactions occurred in 1.6% of adult patients treated with FIASP. In Study A, adult patients with type 1 diabetes mellitus treated with FIASP reported 2.2% injection site reactions. In Study D, infusion site reactions were reported in 10.2% of adult patients with type 1 diabetes mellitus treated with FIASP. In Study E, injection site reactions were reported in 4.2% of pediatric patients with type 1 diabetes mellitus treated with FIASP.

Weight Gain

Weight gain can occur with insulin therapy, including FIASP, and has been attributed to the anabolic effects of insulin and the decrease in glucosuria. In Study A, adult patients with type 1 diabetes mellitus treated with FIASP gained an average of 0.7 kg and in Study B, adult patients with type 2 diabetes mellitus treated with FIASP gained an average of 2.7 kg.

Peripheral Edema

Insulin, including FIASP, may cause sodium retention and edema, particularly if previous poor metabolic control is improved by intensified insulin therapy. In the clinical program, peripheral edema occurred in 0.8% of adult patients treated with FIASP.

6.2 Postmarketing Experience

The following additional adverse reactions have been identified during post-approval use of insulin aspart. Because these reactions are reported voluntarily from a population of uncertain size, it is not always possible to reliably estimate their frequency or establish a causal relationship to drug exposure.

Localized cutaneous amyloidosis at the injection site has occurred. Hyperglycemia has been reported with repeated insulin injections into areas of localized cutaneous amyloidosis; hypoglycemia has been reported with a sudden change to an unaffected injection site.

7 DRUG INTERACTIONS

Table 5 includes clinically significant drug interactions with FIASP.

Table 5. Clinically Significant Drug Interactions with FIASP

Drugs That May Increase the Risk of Hypoglycemia
Drugs: | Antidiabetic agents, ACE inhibitors, angiotensin II receptor blocking agents, disopyramide, fibrates, fluoxetine, monoamine oxidase inhibitors, pentoxifylline, pramlintide, salicylates, somatostatin analogs (e.g., octreotide), and sulfonamide antibiotics.
Intervention: | Dose reductions and increased frequency of glucose monitoring may be required when FIASP is co-administered with these drugs.
Drugs That May Decrease the Blood Glucose Lowering Effect of FIASP
Drugs: | Atypical antipsychotics (e.g., olanzapine and clozapine), corticosteroids, danazol, diuretics, estrogens, glucagon, isoniazid, niacin, oral contraceptives, phenothiazines, progestogens (e.g., in oral contraceptives), protease inhibitors, somatropin, sympathomimetic agents (e.g., albuterol, epinephrine, terbutaline), and thyroid hormones.
Intervention: | Dose increases and increased frequency of glucose monitoring may be required when FIASP is co-administered with these drugs.
Drugs That May Increase or Decrease the Blood Glucose Lowering Effect of FIASP
Drugs: | Alcohol, beta-blockers, clonidine, and lithium salts. Pentamidine may cause hypoglycemia, which may sometimes be followed by hyperglycemia.
Intervention: | Dose adjustment and increased frequency of glucose monitoring may be required when FIASP is co-administered with these drugs.
Drugs That May Blunt Signs and Symptoms of Hypoglycemia
Drugs: | Beta-blockers, clonidine, guanethidine, and reserpine.
Intervention: | Increased frequency of glucose monitoring may be required when FIASP is co-administered with these drugs.

8 USE IN SPECIFIC POPULATIONS

8.1 Pregnancy

Risk Summary

There are no available data with FIASP in pregnant women to inform a drug-associated risk for major birth defects and miscarriage. Available information from published randomized controlled trials with insulin aspart use during the second trimester of pregnancy have not reported an association with insulin aspart and major birth defects or adverse maternal or fetal outcomes [see Data]. There are risks to the mother and fetus associated with poorly controlled diabetes in pregnancy [see Clinical Considerations].

In animal reproduction studies, administration of subcutaneous insulin aspart to pregnant rats and rabbits during the period of organogenesis did not cause adverse developmental effects at exposures 8- times and equal to the human subcutaneous dose of 1.0 unit/kg/day, respectively. Pre- and post-implantation losses and visceral/skeletal abnormalities were seen at higher exposures, which are considered secondary to maternal hypoglycemia. These effects were similar to those observed in rats administered regular human insulin [see Data].

The estimated background risk of major birth defects is 6-10% in women with pre-gestational diabetes with a HbA1c >7% and has been reported to be as high as 20-25% in women with a HbA1c >10%. The estimated background risk of miscarriage for the indicated population is unknown. In the U.S. general population, the estimated background risk of major birth defects and miscarriage in clinically recognized pregnancies is 2-4% and 15-20%, respectively.

Clinical Considerations

Disease-Associated Maternal and/or Embryo-Fetal Risk

Poorly controlled diabetes in pregnancy increases the maternal risk for diabetic ketoacidosis, preeclampsia, spontaneous abortions, preterm delivery, and delivery complications. Poorly controlled diabetes increases the fetal risk for major birth defects, stillbirth, and macrosomia related morbidity.

Data

Human Data

Published data from 5 randomized controlled trials of 441 pregnant women with diabetes mellitus treated with insulin aspart starting during the late 2nd trimester of pregnancy did not identify an association of insulin aspart with major birth defects or adverse maternal or fetal outcomes. However, these studies cannot definitely establish the absence of any risk because of methodological limitations, including a variable duration of treatment and small size of the majority of the trials.

Animal Data

Fertility, embryo-fetal and pre-and postnatal development studies have been performed with insulin aspart and regular human insulin in rats and rabbits. In a combined fertility and embryo-fetal development study in rats, insulin aspart was administered before mating, during mating, and throughout pregnancy. Further, in a pre- and postnatal development study insulin aspart was given throughout pregnancy and during lactation to rats. In an embryo-fetal development study insulin aspart was given to female rabbits during organogenesis. The effects of insulin aspart did not differ from those observed with subcutaneous regular human insulin. Insulin aspart, like human insulin, caused pre- and post-implantation losses and visceral/skeletal abnormalities in rats at a dose of 200 units/kg/day (approximately 32 times the human subcutaneous dose of 1.0 unit/kg/day, based on human exposure equivalents) and in rabbits at a dose of 10 units/kg/day (approximately three times the human subcutaneous dose of 1.0 unit/kg/day, based on human exposure equivalents). No significant effects were observed in rats at a dose of 50 units/kg/day and in rabbits at a dose of 3 units/kg/day. These doses are approximately 8 times the human subcutaneous dose of 1.0 unit/kg/day for rats and equal to the human subcutaneous dose of 1.0 unit/kg/day for rabbits, based on human exposure equivalents. The effects are considered secondary to maternal hypoglycemia.

8.2 Lactation

Risk Summary

There are no data on the presence of FIASP in human milk, the effects on the breastfed infant, or the effect on milk production. One small published study reported that exogenous insulin, including insulin aspart, was present in human milk. However, there is insufficient information to determine the effects of insulin aspart on the breastfed infant and no available information on the effects of insulin aspart on milk production. The developmental and health benefits of breastfeeding should be considered along with the mother’s clinical need for insulin, any potential adverse effects on the breastfed child from FIASP or insulin aspart or from the underlying maternal condition.

8.4 Pediatric Use

The safety and effectiveness of FIASP have been established to improve glycemic control in pediatric patients with diabetes mellitus. Use of FIASP for this indication is supported by evidence from an adequate and well-controlled study in 777 pediatric patients with type 1 diabetes mellitus aged 2 to 17 years, and from studies in adults with diabetes mellitus [see Clinical Pharmacology (12.3) and Clinical Studies (14)].

Pediatric patients with type 1 diabetes mellitus treated with mealtime and postmeal FIASP reported a higher rate of blood glucose confirmed hypoglycemic episodes compared to patients treated with NovoLog; the imbalance was greater during the nocturnal period. Monitor blood glucose levels closely in pediatric patients [see Warnings and Precautions (5.3), Clinical Trial Experience (6.1)].

8.5 Geriatric Use

In the three controlled clinical studies, 192 of 1219 (16%) FIASP treated patients with type 1 or type 2 diabetes mellitus were ≥ 65 years of age and 24 of 1219 (2%) were ≥ 75 years of age. No overall differences in safety or effectiveness were observed between these elderly patients and younger adult patients.

Nevertheless, caution should be exercised when FIASP is administered to geriatric patients. In elderly patients with diabetes, the initial dosing, dose increments, and maintenance dosage should be conservative to avoid hypoglycemia [see Warnings and Precautions (5.3), Adverse Reactions (6.1) and Clinical Studies (14)].

Pharmacokinetic/pharmacodynamic study to assess the effect of age on the onset of FIASP action has been performed [see Clinical Pharmacology (12.3)].

8.6 Renal Impairment

Patients with renal impairment may be at increased risk of hypoglycemia and may require more frequent FIASP dose adjustment and more frequent blood glucose monitoring [see Warnings and Precautions (5.3) and Clinical Pharmacology (12.3)].

8.7 Hepatic Impairment

Patients with hepatic impairment may be at increased risk of hypoglycemia and may require more frequent FIASP dose adjustment and more frequent blood glucose monitoring [see Warnings and Precautions (5.3) and Clinical Pharmacology (12.3)].

10 OVERDOSAGE

Excess insulin administration may cause hypoglycemia and hypokalemia [see Warnings and Precautions (5.3, 5.5)]. Mild episodes of hypoglycemia usually can be treated with oral glucose. Adjustments in drug dosage, meal patterns, or exercise, may be needed. More severe episodes with coma, seizure or neurologic impairment may be treated with an intramuscular/subcutaneous glucagon product for emergency use or concentrated intravenous glucose. Sustained carbohydrate intake and observation may be necessary because hypoglycemia may recur after apparent clinical recovery. Hypokalemia must be corrected appropriately.

11 DESCRIPTION

Insulin aspart is a rapid-acting insulin analog for subcutaneous or intravenous administration. Insulin aspart is homologous with regular human insulin with the exception of a single substitution of the amino acid proline by aspartic acid in position B28, and is produced by recombinant DNA technology utilizing Saccharomyces cerevisiae. Insulin aspart has the empirical formula C256H381N65079S6 and a molecular weight of 5825.8 daltons.

FIASP (insulin aspart) injection is an aqueous, sterile, clear and colorless solution. Each mL contains 100 units of insulin aspart and the inactive ingredients: arginine (as L-arginine hydrochloride), USP (3.48 mg); dibasic sodium phosphate, USP (0.42 mg); glycerin, USP (3.3 mg); metacresol, USP (1.72 mg); niacinamide, USP (20.8 mg); phenol, USP (1.50 mg); zinc (as zinc acetate), USP (19.6 mcg) and Water for Injection. Hydrochloric acid and/or sodium hydroxide may be added to adjust pH to 7.1.

12 CLINICAL PHARMACOLOGY

12.1 Mechanism of Action

The primary activity of FIASP is the regulation of glucose metabolism. Insulins, including insulin aspart, the active ingredient in FIASP, exert their specific action through binding to insulin receptors. Receptor-bound insulin lowers blood glucose by facilitating cellular uptake of glucose into skeletal muscle and adipose tissue and by inhibiting the output of glucose from the liver. Insulin inhibits lipolysis in the adipocyte, inhibits proteolysis, and enhances protein synthesis.

12.2 Pharmacodynamics

The time course of insulin action (i.e., glucose lowering) may vary considerably in different individuals or within the same individual. The average pharmacodynamic profile (i.e., glucose lowering effect measured as glucose infusion rate (GIR) in a euglycemic clamp study) for subcutaneous administration of 0.1, 0.2, and 0.4 unit/kg of FIASP in 46 patients with Type 1 diabetes mellitus is shown in Figure 2 and key characteristics of the timing of the effect are described in Table 6 below.

Table 6. Timing of insulin effect (i.e., mean pharmacodynamic effect) after subcutaneous administration of 0.1, 0.2 and 0.4 unit/kg of FIASP in patients (N=46) with Type 1 Diabetes Mellitus and corresponding to the data shown in Figure 2

Parameter for Insulin Effect | FIASP; 0.1 unit/kg | FIASP; 0.2 unit/kg | FIASP; 0.4 unit/kg
Time to first measurable effect | ~20 minutes | ~17 minutes | ~16 minutes
Time to peak effect | ~91 minutes | ~122 minutes | ~133 minutes
Time for effect to return to baseline | ~5 hours | ~6 hours | ~7 hours

Figure 2. Mean insulin effect (i.e., mean pharmacodynamic effect) over time after subcutaneous administration of 0.1, 0.2 and 0.4 unit/kg of FIASP in patients (N=46) with Type 1 Diabetes Mellitus

On average, the pharmacodynamic effects of FIASP, measured as area under the glucose infusion rate-time curve (AUCGIR), was 697 mg/kg, 1406 mg/kg, and 2427 mg/kg following administration of 0.1, 0.2, and 0.4 unit/kg of FIASP.

The day-to-day variability in glucose-lowering-effect of FIASP within patients was ~18% for total glucose lowering (AUCGIR, 0-12h) and ~19% for maximum glucose lowering effect (GIRmax).

12.3 Pharmacokinetics

Absorption

Pharmacokinetic results from a euglycemic clamp study in adult patients with type 1 diabetes mellitus (N=51) showed that insulin aspart appeared in the circulation ~2.5 minutes after administration of FIASP (Figure 3). Time to maximum insulin concentrations was achieved ~63 minutes after administration of FIASP.

Figure 3. Mean Insulin Aspart Serum Concentration Profile in Adult Subjects with Type 1 Diabetes Mellitus (N=51) following a single 0.2 unit/kg dose (subcutaneous) of FIASP

Total insulin exposure and maximum insulin concentration increase proportionally with increasing subcutaneous dose of FIASP within the therapeutic dose range.

Distribution

Insulin aspart has a low binding affinity to plasma proteins (<10%), similar to that seen with regular human insulin.

Elimination

The apparent terminal half-life after subcutaneous administration of FIASP is about 1.1 hours.

Specific Populations

Age, gender, BMI, and race did not meaningfully affect the pharmacokinetics and pharmacodynamics of FIASP.

Patients with Renal and Hepatic Impairment

Based on studies conducted with insulin aspart, renal and hepatic impairment is not known to impact the pharmacokinetics of insulin aspart.

12.6 Immunogenicity

The observed incidence of anti-drug antibodies is highly dependent on the sensitivity and specificity of the assay. Differences in assay methods preclude meaningful comparisons of the incidence of anti-drug antibodies in the studies described below with the incidence of anti-drug antibodies in other studies, including those of FIASP or of other insulin aspart products.

In a 26-week study in adult subjects with type 1 diabetes mellitus (Study A) [see Clinical Studies (14.2)], among the 763 subjects who received FIASP, 97% were positive for cross-reacting anti-insulin antibodies (AIA) at least once during the study, including 90% that were positive at baseline. A total of 25% of patients who received FIASP were positive for anti-drug (insulin aspart) antibodies (ADA) at least once during the study, including 17% that were positive at baseline.

In a 26-week study in pediatric subjects with type 1 diabetes mellitus (Study E) [see Clinical Studies (14.3)], among the 519 subjects who received FIASP, 97% were positive for cross-reacting AIA at least once during the study, including 95% that were positive at baseline. A total of 19% of patients who received FIASP were positive for ADA at least once during the study, including 16.0% that were positive at baseline.

There was no identified clinically significant effect of ADA on pharmacokinetics, pharmacodynamics, safety, or effectiveness of FIASP.

13 NONCLINICAL TOXICOLOGY

13.1 Carcinogenesis, Mutagenesis, Impairment of Fertility

In 52-week studies, Sprague-Dawley rats were dosed subcutaneously with insulin aspart at 10, 50, and 200 units/kg/day (approximately 2, 8, and 32 times the human subcutaneous dose of 1.0 units/kg/day, based on units/body surface area, respectively). At a dose of 200 units/kg/day, insulin aspart increased the incidence of mammary gland tumors in females when compared to untreated controls. The incidence of mammary tumors for insulin aspart was not significantly different than for regular human insulin. The relevance of these findings to humans is not known.

Insulin aspart was not genotoxic in the following tests: Ames test, mouse lymphoma cell forward gene mutation test, human peripheral blood lymphocyte chromosome aberration test, in vivo micronucleus test in mice, and in ex vivo UDS test in rat liver hepatocytes.

In fertility studies in male and female rats, at subcutaneous doses up to 200 units/kg/day (approximately 32 times the human subcutaneous dose, based on units/body surface area), no direct adverse effects on male and female fertility, or general reproductive performance of animals was observed.

14 CLINICAL STUDIES

14.1 Overview of Clinical Studies

The efficacy of FIASP was evaluated in 3 randomized, active-controlled trials of 18 to 26 weeks duration in adults and one randomized, active-controlled, treat-to-target trial of 26 weeks duration in pediatric patients.

In total 1,224 adult subjects (N=763 with type 1 diabetes mellitus; N=461 with type 2 diabetes mellitus) and 519 pediatric subjects with type 1 diabetes mellitus were randomized to FIASP. In adult and pediatric patients with type 1 diabetes mellitus, mealtime FIASP and postmeal FIASP led to non-inferior glycemic control compared to mealtime NovoLog, both in combination with basal insulin. In adult patients with type 2 diabetes mellitus, mealtime FIASP provided non-inferior glycemic control compared to mealtime NovoLog, both in combination with metformin. In addition, mealtime FIASP in a basal-bolus regimen with metformin also provided statistically significant improvement in the overall glycemic control compared to basal insulin therapy alone with metformin in adult patients with type 2 diabetes mellitus.

In adults with type 1 diabetes mellitus (N=472), FIASP led to non-inferior glycemic control compared to NovoLog when both were administered by continuous subcutaneous insulin infusion (CSII) pump.

14.2 Type 1 Diabetes Mellitus - Adults

Study A (NCT01831765): FIASP added to insulin detemir in adult patients with Type 1 Diabetes Mellitus inadequately controlled at baseline.

The efficacy of FIASP was evaluated in a 26-week, randomized, active controlled, treat-to-target, multicenter trial in 1,143 adult patients with type 1 diabetes mellitus inadequately controlled at baseline. Patients were randomized to either blinded mealtime FIASP (N=381), blinded mealtime NovoLog (N=380), or open-label postmeal FIASP (N=382), all in combination with once or twice daily insulin detemir. At randomization, patients were switched to FIASP on a unit to unit basis. Mealtime FIASP or NovoLog was injected 0-2 minutes before the meal, and postmeal FIASP was injected 20 minutes after the start of the meal.

The mean age of the randomized subjects was 44.4 years and mean duration of diabetes was 19.9 years. 59% were male, 93% were White and 2% were Black or African American; and 7% were Hispanic or Latino. The mean BMI was 26.7 kg/m^2.

After 26 weeks of treatment, treatment difference in HbA1c reduction from baseline between mealtime FIASP compared to mealtime NovoLog, and the treatment difference between postmeal FIASP compared to mealtime NovoLog met the pre-specified non-inferiority margin (0.4%). See Table 7. Insulin doses were similar among study arms at baseline and at the end of the trial.

Table 7. Results from Study A: 26-Week Trial of Mealtime FIASP and Postmeal FIASP compared to Mealtime NovoLog Used in Combination with Insulin Detemir in Adults with Type 1 Diabetes Mellitus

 | Mealtime FIASP; + insulin detemir | Postmeal FIASP; + insulin detemir | Mealtime NovoLog; + insulin detemir
Number of subjects randomized (N) | 381 | 382 | 380
HbA1c (%)
Baseline (mean) | 7.6 | 7.6 | 7.6
Adjusted mean change from baseline | -0.32 | -0.13 | -0.17
Estimated treatment difference vs. mealtime NovoLog [95% CI]* | -0.15 [-0.23;-0.07] | 0.04 [-0.04;0.12]

Baseline is based on the mean of the observed last available values prior to randomization.

*Tested for non-inferiority

Estimated treatment difference was calculated using mixed model for repeated measurements (MMRM).

7.6% of subjects on the Mealtime FIASP arm, 7.6% of subjects on the Postmeal FIASP arm, and 5.3% of subjects on the Mealtime NovoLog arm were missing the final HbA1c assessment.

14.3 Type 1 Diabetes Mellitus - Pediatric Patients

Study E (NCT02670915): FIASP added to insulin degludec in pediatric patients with Type 1 Diabetes Mellitus.

The efficacy of FIASP was evaluated in a 26-week, randomised, multinational, active controlled, treat-to-target, 3-armed parallel-group trial in 777 pediatric patients with type 1 diabetes mellitus. Patients were randomized to either blinded mealtime FIASP (N=260), blinded mealtime NovoLog (N=258), or open-label postmeal FIASP (N=259), all in combination with once daily insulin degludec. Mealtime FIASP or NovoLog was injected 0-2 minutes before the meal, and postmeal FIASP was injected 20 minutes after the start of the meal.

The mean age of the subjects at baseline was 11.7 years (range 2 to 17 years) and the mean duration of diabetes was 4.4 years. 54% were male, 81% were White, 16% were Asian and 2% were Black or African American. The mean BMI was 19.7 kg/m^2.

After 26 weeks of treatment, the treatment difference for change in HbA1c from baseline between mealtime FIASP compared to mealtime NovoLog, and the treatment difference between postmeal FIASP compared to mealtime NovoLog met the pre-specified non-inferiority margin (0.4%). See Table 8. Insulin doses were similar among study arms at baseline and at the end of the trial.

Table 8. Results from Study E: 26-Week Trial of Mealtime FIASP and Postmeal FIASP compared to Mealtime NovoLog Used in Combination with Insulin Degludec in Pediatrics with Type 1 Diabetes Mellitus

 | Mealtime FIASP; + insulin degludec | Postmeal FIASP; + insulin degludec | Mealtime NovoLog; + insulin degludec
Number of subjects randomized (N) | 260 | 259 | 258
HbA1c (%)
Baseline (mean) | 7.57 | 7.58 | 7.53
Adjusted mean change from baseline | 0.06 | 0.35 | 0.22
Estimated treatment difference vs. mealtime NovoLog [95% CI]* | -0.17 [-0.30; -0.03] | 0.13 [-0.01; 0.26]

Baseline is based on the mean of the observed last available values prior to randomization.

*Tested for non-inferiority

Estimated treatment difference was calculated using ANCOVA. Week 26, change in HbA1c was missing for 1.5%, 1.9%, and 1.6% of subjects in mealtime FIASP, post-meal FIASP, and NovoLog respectively. Missing values were imputed with a missing at random assumption.

14.4 Type 2 Diabetes Mellitus - Adults

Study B (NCT01819129): FIASP added to basal insulin and oral antidiabetics in patients with Type 2 Diabetes Mellitus inadequately controlled at baseline on basal insulin and oral antidiabetics

The efficacy of FIASP was evaluated in a 26-week randomized, double-blind, active controlled, treat-to-target, multicenter, multinational, parallel group trial in 689 adult patients with type 2 diabetes mellitus who were inadequately controlled at baseline on basal insulin and oral antidiabetic therapy and had been on these therapies for at least 6 months. Patients were randomized to either mealtime FIASP or to mealtime NovoLog, both in combination with insulin glargine and metformin in a basal-bolus regimen. Mealtime FIASP or mealtime NovoLog was injected 0-2 minutes before the meal.

The mean age of the randomized subjects was 59.5 years and the mean duration of diabetes was 12.7 years. 49% were male, 81% were White, and 6% were Black or African American; and 6% were Hispanic or Latino. The mean BMI was 31.2 kg/m^2.

After 26 weeks of treatment, the treatment difference in HbA1c reduction from baseline between mealtime FIASP and mealtime NovoLog, both in combination with insulin glargine and metformin, met the pre-specified non-inferiority margin (0.4%). See Table 9. Insulin doses were similar among study arms at the end of the trial.

Table 9. Results from Study B: 26-Week Trial of Mealtime FIASP Compared to Mealtime NovoLog, Both used in Combination with Insulin Glargine and Metformin, in Adults with Type 2 Diabetes Mellitus

 | Mealtime FIASP; +insulin glargine; +metformin | Mealtime NovoLog; +insulin glargine; +metformin
Number of subjects randomized (N) | 345 | 344
HbA1c (%)
Baseline | 8.0 | 7.9
Adjusted change from baseline | -1.38 | -1.36
Estimated treatment difference vs. NovoLog [95%CI]* | -0.02 [-0.15;0.10]

Baseline is based on the mean of the observed last available values prior to randomization.

*Tested for non-inferiority

Estimated treatment difference was calculated using mixed model for repeated measurements (MMRM).

11.9% of subjects on the Mealtime FIASP arm and 10.2% of subjects on the Mealtime NovoLog arm were missing the final HbA1c assessment.

Study C (NCT01850615): FIASP added to basal insulin and metformin in patients with Type 2 Diabetes Mellitus inadequately controlled at baseline on basal insulin and metformin

The efficacy of FIASP was evaluated in an 18-week randomized, open-label, parallel group trial in 236 adult patients with type 2 diabetes mellitus who were inadequately controlled on basal insulin and metformin therapy, either with or without other oral antidiabetic therapy, for at least 3 months. Patients were randomized to either mealtime FIASP in addition to basal insulin and metformin or to continuing basal insulin and metformin therapy without FIASP. The basal insulins used in both treatment arms were insulin glargine, insulin detemir or NPH. All patients were also required to be on ≥1000 mg metformin treatment at baseline.

The mean age of the trial population was 57.4 years and the mean duration of diabetes was 11years. 48% were male, 70% were White and 4% were Black or African American; and 37% were Hispanic or Latino. The mean BMI was 30.8 kg/m^2.

After 18 weeks of treatment, addition of FIASP to basal insulin and metformin statistically significantly reduced HbA1c compared to continuing basal insulin and metformin therapy without addition of FIASP (Table 10).

Table 10. Results from Study C: 18-Week Trial of Mealtime FIASP in Adults with Type 2 Diabetes Mellitus Inadequately Controlled at Baseline on Basal Insulin and Metformin

 | FIASP + basal insulin + metformin | Basal insulin + metformin
Number of subjects randomized (N) | 116 | 120
HbA1c (%)
Baseline | 7.9 | 7.9
Adjusted change from baseline | -1.16 | -0.22
Estimated treatment difference vs. basal insulin+metformin [95%CI] | -0.94 [-1.17; -0.72]*
Proportion of patients Achieving HbA1c < 7% at Trial End | 60.3% | 18.3%

Baseline is based on the mean of the observed last available values prior to randomization.

*p<0.0001, 1-sided p-value evaluated at 2.5% level for superiority.

Estimated treatment difference was calculated using mixed model for repeated measurements (MMRM).

6.0% of subjects on the mealtime FIASP arm and 3.3% of subjects on the placebo arm were missing the final HbA1c assessment.

14.5 Type 1 Diabetes Mellitus– Adult Continuous Subcutaneous Insulin Infusion (CSII)

Study D (NCT02825251): FIASP in Continuous Subcutaneous Insulin Infusion (CSII) in Adults with Type 1 Diabetes Mellitus

The efficacy and safety of FIASP vs. NovoLog in CSII in adult subjects with type 1 diabetes mellitus (N=472) was evaluated in a randomized, multicenter, multinational, active controlled, treat-to-target, parallel group trial with a 4-week run-in and a 16-week treatment period. Meal-time bolus insulin infusion was initiated 0-2 minutes before a meal.

The mean age of the randomized subjects was 43 years and the mean duration of diabetes was 24 years. 43% were male. 89% were White, 1% were Black or African American, and 1% were Asian; and 3% were Hispanic or Latino. The mean BMI was 26.3 kg/m^2.

After 16 weeks of treatment, the treatment difference in HbA1c reduction from baseline between FIASP and NovoLog was 0.10 with 95%CI [0.02, 0.18] (Table 11).

Table 11. Results from Study D: 16-Week Trial FIASP in Adults with Type 1 Diabetes

 | FIASP | NovoLog
Number of subjects randomized (N) | 236 | 236
HbA1c (%)
Baseline | 7.5 | 7.5
Adjusted change from baseline | -0.04 | -0.14
Estimated treatment difference FIASP vs. NovoLog [95%CI]* | 0.10 [0.02; 0.18]
Proportion of patients Achieving HbA1c < 7% at Trial End | 20.3% | 23.3%

Baseline is based on the mean of the observed last available values prior to randomization.

*Tested for non-inferiority using a margin of 0.4%.

Estimated treatment difference was calculated using ANCOVA.

2.1% of subjects on the FIASP arm and 2.5% of subjects on the NovoLog arm were missing the final HbA1c assessment. Missing values were imputed using multiple imputation with a mean equal to the baseline value of the corresponding patient.

16 HOW SUPPLIED/STORAGE AND HANDLING

16.1 How Supplied

FIASP (insulin aspart) injection 100 units of insulin aspart per mL (U-100) is available as a clear and colorless solution in the following presentations and packaging configurations:

Carton of one 10 mL multiple-dose vials NDC 0169-3201-11
Carton of five 3 mL single-patient-use FIASP FlexTouch pens NDC 0169-3204-15
Carton of five 3 mL single-patient-use PenFill cartridges* NDC 0169-3205-15
Carton of five 1.6 mL single-patient-use PumpCart cartridges** NDC 0169-3206-15
The FIASP FlexTouch pen dials in 1 unit increments.
* FIASP PenFill cartridges are designed for use with Novo Nordisk insulin delivery devices.
** FIASP PumpCart cartridges are designed for use in compatible pumps only.

16.2 Recommended Storage

Dispense in the original sealed carton with the enclosed Instructions for Use.

Unused FIASP vials should be stored between 2° to 8°C (36° to 46°F) in a refrigerator, but not in or near a freezing compartment. FIASP should not be exposed to excessive heat or light and must never be frozen. Do not use FIASP if it has been frozen. FIASP should not be drawn into a syringe and stored for later use.

Keep the cap on the pen in order to protect from light. Remove the needle from the FIASP FlexTouch pen after each injection and store without a needle attached. Use a new needle for each injection. Keep unused vials, FIASP FlexTouch, PenFill Cartridges and PumpCart cartridges in the carton so they will stay clean and protected from light.

The storage conditions for vials, FIASP FlexTouch pens, 3 mL PenFill cartridges and 1.6 mL PumpCart cartridges are summarized in Table 12:

Table 12. Storage Conditions for Vial, FIASP FlexTouch, PenFill Cartridges

and PumpCart Cartridges

FIASP; presentation | Not in-use (unopened) |  | In-use (opened)
 | Room Temperature (up to 30°C [86°F]) | Refrigerated; (2°C to 8°C [36°F to 46°F]) | Room Temperature (up to 30°C [86°F]) | Refrigerated; (2°C to 8°C [36°F to 46°F])
10 mL multiple-dose vial | 28 days | Until expiration date | 28 days*; (up to 30°C [86°F]) | 28 days*
3 mL single-patient-use FIASP FlexTouch pen | 28 days | Until expiration date | 28 days; (up to 30°C [86°F]) | 28 days
3 mL single-patient-use PenFill cartridges | 28 days | Until expiration date | 28 days; (up to 30°C [86°F]) | Do not refrigerate
1.6 mL single-patient-use PumpCart cartridges | 18 days** | Until expiration date | 4 days**; (up to 37°C [98.6°F]) | Do not refrigerate

*Pump Reservoir: The total in use time is 28 days, including 6 days in the pump reservoir

**PumpCart Cartridges: The maximum time at room temperature is 18 days including 4 days in the pump

Storage of FIASP in Insulin Pump:

- Change FIASP in the pump reservoir at least every 6 days or according to the pump user manual, whichever is shorter.
- Replace the FIASP PumpCart cartridge at least every 4 days or according to the pump user manual, whichever is shorter.
- Change FIASP to avoid insulin degradation or after exposure to temperatures that exceed 37°C (98.6°F).
- The infusion set and infusion set insertion sites should be changed according to the manufacturers’ user manual.

Storage of FIASP in Intravenous Infusion Fluids:
Infusion bags prepared as indicated under Dosage and Administration (2.2) are stable at room temperature at 20°C to 25°C (68°F to 77°F) for 24 hours.

17 PATIENT COUNSELING INFORMATION

Advise the patient to read the FDA-Approved Patient Labeling (Patient Information and Instructions for Use).

Never Share a FIASP FlexTouch Pen Device, PenFill Cartridge or PenFill Cartridge Device Between Patients

Advise patients that they should never share a FIASP FlexTouch pen device, PenFill cartridge or PenFill cartridge devices with another person, even if the needle is changed, because doing so carries a risk for transmission of blood-borne pathogens. Advise patients using FIASP vials not to share needles or syringes with another person. Sharing poses a risk for transmission of blood-borne pathogens [see Warnings and Precautions (5.1)].

Hyperglycemia or Hypoglycemia

Inform patients that hypoglycemia is the most common adverse reaction with insulin. Instruct patients on self-management procedures including glucose monitoring, proper injection technique, and management of hypoglycemia and hyperglycemia, especially at initiation of FIASP therapy. Instruct patients on handling of special situations such as intercurrent conditions (illness, stress, or emotional disturbances), an inadequate or skipped insulin dose, inadvertent administration of an increased insulin dose, inadequate food intake, and skipped meals. Instruct patients on the management of hypoglycemia [see Warnings and Precautions (5.3)].

Inform patients that their ability to concentrate and react may be impaired as a result of hypoglycemia. Advise patients who have frequent hypoglycemia or reduced or absent warning signs of hypoglycemia to use caution when driving or operating machinery.

Advise patients that changes in insulin regimen can predispose to hyperglycemia or hypoglycemia and that changes in insulin regimen should be made under close medical supervision [see Warnings and Precautions (5.2)].

Hypersensitivity Reactions

Advise patients that hypersensitivity reactions have occurred with FIASP. Inform patients on the symptoms of hypersensitivity reactions [see Warnings and Precautions (5.6)].

Hypoglycemia due to Medication Errors

Instruct patients to always check the insulin label before each injection to avoid mix-ups between insulin products.

Patients Using Continuous Subcutaneous Insulin Pumps

- Train patients in intensive insulin therapy with multiple injections and in the function of their pump and pump accessories.
- Instruct patients to follow healthcare provider recommendations when setting basal and meal time infusion rate.
- Refer to the continuous subcutaneous infusion pump user manual to see if FIASP can be used with the pump. See recommended reservoir and infusion sets in the insulin pump user manual.
- Instruct patients to change FIASP in the pump reservoir at least every 6 days, or replace the PumpCart cartridge at least every 4 days or according to the pump user manual, whichever is shorter; infusion sets and infusion set insertion sites should be changed in accordance with the manufacturers’ user manual. By following this schedule, patients avoid insulin degradation, infusion set occlusion, and loss of the insulin preservative.
- Instruct patients to discard insulin exposed to temperatures higher than 37°C (98.6°F).
- Instruct patients to inform physician and select a new site for infusion if infusion site becomes erythematous, pruritic, or thickened.
- Instruct patients on the risk of rapid hyperglycemia and ketosis due to pump malfunction, infusion set occlusion, leakage, disconnection or kinking, and degraded insulin. Instruct patients on the risk of hypoglycemia from pump malfunction. If these problems cannot be promptly corrected, instruct patients to resume therapy with subcutaneous insulin injection and contact their physician [see Warnings and Precautions (5) and How Supplied/Storage and Handling (16.2)].

Version: 8

Novo Nordisk®, FIASP®, NovoLog®, FlexTouch®, PenFill® and PumpCart® are registered trademarks of Novo Nordisk A/S.

PATENT Information: http://novonordisk-us.com/products/product-patents.html

© 2023

Manufactured by:

Novo Nordisk Inc.
800 Scudders Mill Road
Plainsboro, New Jersey 08536
U.S. License 1261

For information about FIASP contact:
Novo Nordisk Inc.
800 Scudders Mill Road
Plainsboro, New Jersey 08536
1-800-727-6500

www.novonordisk-us.com

Patient Information

FIASP® (fee’ asp)
(insulin aspart)

Injection, for subcutaneous or intravenous use

Do not share your FIASP with other people, even if the needle has been changed. You may give other people a serious infection, or get a serious infection from them.

What is FIASP?

- FIASP is a man-made insulin that is used to control high blood sugar in adults and children with diabetes mellitus.

Who should not take FIASP?
Do not take FIASP if you:

- are having an episode of low blood sugar (hypoglycemia).
- have an allergy to insulin aspart or any of the ingredients in FIASP.

Before taking FIASP, tell your healthcare provider about all your medical conditions including, if you:

- have kidney problems.
- have liver problems.
- are pregnant or plan to become pregnant. Talk with your healthcare provider about the best way to control your blood sugar if you plan to become pregnant or while you are pregnant.
- are breastfeeding or plan to breastfeed. It is not known if FIASP passes into your breast milk. Talk with your healthcare provider about the best way to feed your baby while using FIASP.
- are taking new prescription or over-the-counter medicines, vitamins, or herbal supplements.

Before you start taking FIASP, talk to your healthcare provider about low blood sugar and how to manage it.

How should I take FIASP?

- Read the Instructions for Use that come with your FIASP.
- Take FIASP exactly as your healthcare provider tells you to.
- FIASP starts acting fast. You should take your dose of FIASP at the beginning of the meal or within 20 minutes after starting a meal.
- Know the type and strength of insulin you take. Do not change the type of insulin you take unless your healthcare provider tells you to. The amount of insulin and the best time for you to take your insulin may need to change if you take different types of insulin.
- If you miss a dose of FIASP, monitor your blood sugar levels to decide if an insulin dose is needed. Continue with your regular dosing schedule at the next meal.
- Check your blood sugar levels. Ask your healthcare provider what your blood sugars should be and when you should check your blood sugar levels.
- Do not reuse or share needles with other people. You may give other people a serious infection or get a serious infection from them.
- FIASP can be injected under the skin (subcutaneously) of your stomach area, upper legs, or upper arms, or by continuous infusion under the skin (subcutaneously) through an insulin pump into an area of your body recommended in the instructions that come with your insulin pump.
- Change (rotate) your injection sites within the area you choose with each dose to reduce your risk of getting pits in skin or thickened skin (lipodystrophy) and skin with lumps (localized cutaneous amyloidosis) at the injection sites.
- Do not use the exact same spot for each injection.
- Do not inject where the skin has pits, is thickened, or has lumps.
- Do not inject where the skin is tender, bruised, scaly or hard, or into scars or damaged skin.

What should I avoid while taking FIASP?
While taking FIASP do not:

- Drive or operate heavy machinery until you know how FIASP affects you.
- Drink alcohol or use prescription or over-the-counter medicines that contain alcohol.

What are the possible side effects of FIASP?
FIASP may cause serious side effects that can lead to death, including:

- low blood sugar (hypoglycemia). Signs and symptoms that may indicate low blood sugar include:

- dizziness or light-headedness

- blurred vision

- anxiety, irritability, or mood changes

- sweating

- slurred speech

- hunger

- confusion

- shakiness

- headache

- fast heart beat

- low potassium in your blood (hypokalemia).
- serious allergic reactions (whole body reactions). Get emergency medical help right away, if you have any of these signs or symptoms of a severe allergic reaction:
  - a rash over your whole body, trouble breathing, a fast heartbeat, swelling of your face, tongue or throat, sweating, extreme drowsiness, dizziness, confusion.
- heart failure. Taking certain diabetes pills called TZDs (thiazolidinediones) with FIASP may cause heart failure in some people. This can happen even if you have never had heart failure or heart problems before. If you already have heart failure it may get worse while you take TZDs with FIASP. Your healthcare provider should monitor you closely while you are taking TZDs with FIASP. Tell your healthcare provider if you have any new or worse symptoms of heart failure including shortness of breath, swelling of your ankles or feet, sudden weight gain. Treatment with TZDs and FIASP may need to be adjusted or stopped by your healthcare provider if you have new or worse heart failure.

Your insulin dose may need to change because of:

- change in level of physical activity or exercise

- increased stress

- change in diet

- weight gain or loss

- illness

Common side effects of FIASP may include:

- skin problems such as eczema, rash, itching, redness and swelling of your skin (dermatitis)
- reactions at the injection site such as itching, rash
- skin thickening or pits at the injection site (lipodystrophy)
- weight gain

These are not all the possible side effects of FIASP. Call your doctor for medical advice about side effects. You may report side effects to FDA at 1-800-FDA-1088.

General information about the safe and effective use of FIASP.

Medicines are sometimes prescribed for purposes other than those listed in a Patient Information leaflet. You can ask your pharmacist or healthcare provider for information about FIASP that is written for health professionals. Do not use FIASP for a condition for which it was not prescribed. Do not give FIASP to other people, even if they have the same symptoms that you have. It may harm them.

What are the ingredients in FIASP?

Active Ingredient: insulin aspart

Inactive Ingredients: arginine, dibasic sodium phosphate, glycerin, metacresol, niacinamide, phenol, zinc and water for injection.

Manufactured by:
Novo Nordisk Inc.

U.S. License Number 1261

For more information, go to www.novonordisk-us.com or call 1-800-727-6500.

This Patient Information has been approved by the U.S. Food and Drug Administration.

Revised: 06/2023

INSTRUCTIONS FOR USE

FIASP (fee’ asp)

(insulin aspart) injection

10 mL multiple-dose vial (100 units/mL, U-100)

Read this Instructions for Use before you start taking FIASP and each time you get a refill. There may be new information. This information does not take the place of talking to your healthcare provider about your medical condition or your treatment. The vial is not recommended for use by the blind or visually impaired without the assistance of a person trained in the proper use of the product and insulin syringe.

Do not reuse or share syringes or needles with other people. You may give other people a serious infection or get a serious infection from them.

Supplies you will need to give your FIASP injection:

- a 10 mL FIASP vial
- a U-100 insulin syringe and needle
- 2 alcohol swabs
- 1 sharps container for throwing away used needles and syringes. See “Disposing of your used needles and syringes” at the end of these instructions.

Preparing your FIASP dose:

- Do not roll or shake the FIASP vial. Shaking the FIASP vial right before the dose is drawn into the syringe may cause bubbles or foam. This can cause you to draw up the wrong dose of insulin.
- The tamper-resistant cap should not be loose or damaged before the first use. Do not use if the tamper-resistant cap is loose or damaged before using FIASP for the first time.
- Wash your hands with soap and water.
- Before you start to prepare your injection, check the FIASP label to make sure that you are taking the right type of insulin. This is especially important if you use more than 1 type of insulin.
- Check that the FIASP vial is not cracked or damaged. Do not use if the FIASP vial is cracked or damaged.
- FIASP should look clear and colorless. Do not use FIASP if it is thick, cloudy, or is colored.
- Do not use FIASP past the expiration date printed on the label.

Step 1: Pull off the tamper-resistant cap (See Figure A).

Step 2: Wipe the rubber stopper with an alcohol swab (See Figure B).

(Figure A Figure B)

Step 3: Hold the syringe with the needle pointing up. Pull down on the plunger until the tip of the plunger reaches the line for the number of units for your prescribed dose (See Figure C).

(Figure C)

Step 4: Push the needle through the rubber stopper of the FIASP vial (See Figure D).

(Figure D)

Step 5: Push the plunger all the way in. This puts air into the FIASP vial (See Figure E).

(Figure E)

Step 6: Turn the FIASP vial and syringe upside down and slowly pull the plunger down until the tip of the plunger is a few units past the line for your dose (See Figure F).

If there are air bubbles, tap the syringe gently a few times to let any air bubbles rise to the top (See Figure G).

(Figure F)

(Figure G)

Step 7: Slowly push the plunger up until the tip of the plunger reaches the line for your prescribed FIASP dose (See Figure H).

(Figure H)

Step 8: Check the syringe to make sure you have the right dose of FIASP.

Step 9: Pull the syringe out of the rubber stopper on the vial (See Figure I).

(Figure I)

Giving your FIASP injection:

- Inject your FIASP exactly as your healthcare provider has shown you. Your healthcare provider should tell you if you need to pinch the skin before injecting.
- You should take your dose of FIASP at the start of a meal or within 20 minutes after starting a meal.
- FIASP can be injected under the skin (subcutaneously) of your stomach area, upper legs, or upper arms, infused in an insulin pump into an area of your body recommended in the instructions that come with your insulin pump, or given through a needle in your arm (intravenously) by your healthcare provider. Do not inject FIASP into your muscle.
- If you use FIASP in an insulin pump, you should change the infusion sets and the infusion set insertion site according to the pump manufacturers’ user manual. The insulin in the reservoir should be changed at least every 6 days even if you have not used all of the insulin.
- If you use FIASP in an insulin pump, see your insulin pump manual for instructions or talk to your healthcare provider. Your healthcare provider should provide recommendations for appropriate basal and meal time infusion rates.
- Change (rotate) your injection sites within the area you choose for each dose to reduce your risk of getting lipodystrophy (pits in skin or thickened skin) and localized cutaneous amyloidosis (skin with lumps) at the injection sites. Do not use the same injection site for each injection. Do not inject where the skin has pits, is thickened, or has lumps. Do not inject where the skin is tender, bruised, scaly or hard, or into scars or damaged skin.
- Do not dilute or mix FIASP with any other type of insulin products or solutions.

Step 10: Choose your injection site (thighs, upper arms, or

abdomen) and wipe the skin with an alcohol swab (See Figure J). Let the injection site dry before you inject your dose.

(Figure J)

Step 11: Insert the needle into your skin. Push down on the plunger to inject your dose (See Figure K).

Make sure you have injected all the insulin in the syringe.

(Figure K)

Step 12: Pull the needle out of your skin. After your injection you may see a drop of FIASP at the needle tip. This is normal and does not affect the dose you just received (See Figure L).

- If you see blood after you take the needle out of your skin, press the injection site lightly with a piece of gauze or an alcohol swab. Do not rub the area.

(Figure L)

After your injection:

- Do not recap the needle. Recapping the needle can lead to needle stick injury.

Disposing of your used needles and syringes:

Put your used insulin needles and syringes in a FDA-cleared sharps disposal container right away after use. Do not throw away (dispose of) loose needles and syringes in your household trash.

If you do not have a FDA-cleared sharps disposal container, you may use a household container that is:

- made of a heavy-duty plastic;
- can be closed with a tight-fitting, puncture-resistant lid, without sharps being able to come out;
- upright and stable during use;
- leak-resistant, and
- properly labeled to warn of hazardous waste inside the container.
- When your sharps disposal container is almost full, you will need to follow your community guidelines for the right way to dispose of your sharps disposal container. There may be state or local laws about how you should throw away used needles and syringes. Do not reuse or share needles or syringes with another person. For more information about safe sharps disposal, and for specific information about sharps disposal in the state that you live in, go to the FDA’s website at: http://www.fda.gov/safesharpsdisposal.
- Do not dispose of your used sharps disposal container in your household trash unless your community guidelines permit this. Do not recycle your used sharps disposal container.

How should I store FIASP?

- Do not freeze FIASP. Do not use FIASP if it has been frozen.
- Keep FIASP away from excessive heat or light.

All unopened vials:

- Store unopened FIASP vials in the refrigerator at 36°F to 46°F (2°C to 8°C) or at room temperature below 86°F (30°C).
- If unopened vials have been stored in the refrigerator, vials may be used until the expiration date printed on the label.
- If unopened vials have been stored at room temperature, vials should be thrown away after 28 days.

After vials have been opened:

- Opened FIASP vials can be stored in the refrigerator at 36°F to 46°F (2°C to 8°C) or at room temperature below 86°F (30°C).
- Throw away all opened FIASP vials after 28 days (including 6 days pump in-use time), even if they still have insulin left in them.

General information about the safe and effective use of FIASP

- Always use a new syringe and needle for each injection to help ensure sterility and prevent blocked needles.
- Do not reuse or share syringes or needles with other people. You may give other people a serious infection or get a serious infection from them.
- Keep FIASP vials, syringes, and needles out of the reach of children.

This Instructions for Use has been approved by the U.S. Food and Drug Administration.

Manufactured by:

Novo Nordisk Inc.

800 Scudders Mill Road

Plainsboro, NJ 08536

1-800-727-6500

U.S. License No. 1261

FIASP® is a registered trademark of Novo Nordisk A/S.

PATENT Information: http://novonordisk-us.com/products/product-patents.html

© 2023 Novo Nordisk

For information about FIASP® contact:

Novo Nordisk Inc.

800 Scudders Mill Road

Plainsboro, New Jersey 08536

1-800-727-6500

www.novonordisk-us.com

Revised: 06/2023

INSTRUCTIONS FOR USE

FIASP® [fee’ asp] FlexTouch®

(insulin aspart)

injection, for subcutaneous use

3 mL single-patient-use pen: 100 units/mL (U-100)

- Do not share your FIASP FlexTouch Pen with other people, even if the needle is changed. You may give other people a serious infection, or get a serious infection from them.
- FIASP FlexTouch Pen (“Pen”) is a prefilled disposable, single-patient-use pen containing 300 units of U-100 FIASP (insulin aspart) injection. You can inject from 1 to 80 units in a single injection. The units can be increased by 1 unit at a time.
- People who are blind or have vision problems should not use the Pen without help from a person trained to use the Pen.
- Do not use a syringe to remove FIASP from the FlexTouch Pen.

Supplies you will need to give your FIASP injection:

- FIASP FlexTouch Pen
- a new NovoFine, NovoFine Plus or NovoTwist needle
- alcohol swab
- a sharps container for throwing away used Pens and needles. See “After your injection” at the end of these instructions.

Preparing your FIASP FlexTouch Pen:

- Wash your hands with soap and water.
- Before you start to prepare your injection, check the FIASP FlexTouch Pen label to make sure you are taking the right type of insulin. This is especially important if you take more than 1 type of insulin.
- FIASP should look clear and colorless. Do not use FIASP if it is thick, cloudy, or is colored.
- Do not use FIASP past the expiration date printed on the label or 28 days after you start using the Pen.
- Always use a new needle for each injection to help ensure sterility and prevent blocked needles. Do not reuse or share needles with another person. You may give other people a serious infection, or get a serious infection from them.

Step 1:

- Pull Pen cap straight off (See Figure B).

Step 2:

- Check the liquid in the Pen (See Figure C). FIASP should look clear and colorless. Do not use it if it looks cloudy or colored.

Step 3:

- Select a new needle.
- Pull off the paper tab from the outer needle cap (See Figure D).

Step 4:

- Push the capped needle straight onto the Pen and twist the needle on until it is tight (See Figure E).

Step 5:

- Pull off the outer needle cap. Do not throw it away (See Figure F).

Step 6:

- Pull off the inner needle cap and throw it away (See Figure G).

Priming your FIASP FlexTouch Pen:

Step 7:

- Turn the dose selector to select 2 units (See Figure H).

Step 8:

- Hold the Pen with the needle pointing up. Tap the top of the Pen gently a few times to let any air bubbles rise to the top (See Figure I).

Step 9:

- Hold the Pen with the needle pointing up. Press and hold in the dose button until the dose counter shows “0”. The “0” must line up with the dose pointer.
- A drop of insulin should be seen at the needle tip (See Figure J).
- If you do not see a drop of insulin, repeat steps 7 to 9, no more than 6 times.
- If you still do not see a drop of insulin, change the needle and repeat steps 7 to 9.

Selecting your dose:

Step 10:

Check to make sure the dose selector is set at 0.

- Turn the dose selector to select the number of units you need to inject. The dose pointer should line up with your dose (See Figure K).
- If you select the wrong dose, you can turn the dose selector forwards or backwards to the correct dose.
- The even numbers are printed on the dial.
- The odd numbers are shown as lines.

- The FIASP FlexTouch Pen insulin scale will show you how much insulin is left in your Pen (See Figure L).

- To see how much insulin is left in your FIASP FlexTouch Pen:
- Turn the dose selector until it stops. The dose counter will line up with the number of units of insulin that is left in your Pen. If the dose counter shows 80, there are at least 80 units left in your Pen.
- If the dose counter shows less than 80, the number shown in the dose counter is the number of units left in your Pen.

Giving your injection:

- Inject your FIASP exactly as your healthcare provider has shown you. Your healthcare provider should tell you if you need to pinch the skin before injecting.
- You should take your dose of FIASP at the start of a meal or within 20 minutes after starting a meal.
- FIASP can be injected under the skin (subcutaneously) of your stomach area (abdomen), upper legs (thighs) or upper arms. Do not inject FIASP into your muscle.
- Change (rotate) your injection sites within the area you choose for each dose to reduce your risk of getting lipodystrophy (pits in skin or thickened skin) and localized cutaneous amyloidosis (skin with lumps) at the injection sites. Do not use the same injection site for each injection. Do not inject where the skin has pits, is thickened, or has lumps. Do not inject where the skin is tender, bruised, scaly or hard, or into scars or damaged skin.

Step 11:

- Choose your injection site (thighs, upper arms, or abdomen) and wipe the skin with an alcohol swab. Let the injection site dry before you inject your dose (See Figure M).

Step 12:

- Insert the needle into your skin (See Figure N).
  - Make sure you can see the dose counter. Do not cover it with your fingers; this can stop your injection.

Step 13:

- Press and hold down the dose button until the dose counter shows “0” (See Figure O).
  - The “0” must line up with the dose pointer. You may then hear or feel a click.
- Keep the needle in your skin after the dose counter has returned to “0” and slowly count to 6 (See Figure P).
  - When the dose counter returns to “0”, you will not get your full dose until 6 seconds later.
  - If the needle is removed before you count to 6, you may see a stream of insulin coming from the needle tip.
  - If you see a stream of insulin coming from the needle tip you will not get your full dose. If this happens you should check your blood sugar levels more often because you may need more insulin.

Step 14:

- Pull the needle out of your skin (See Figure Q).
  - If you see blood after you take the needle out of your skin, press the injection site lightly with a piece of gauze or an alcohol swab. Do not rub the area.

Step 15:

- Carefully remove the needle from the Pen and throw it away (See Figure R).
  - Do not recap the needle. Recapping the needle can lead to needle stick injury.
- If you do not have a sharps container, carefully slip the needle into the outer needle cap (See Figure S). Safely remove the needle and throw it away as soon as you can.
  - Do not store the Pen with the needle attached. Storing without the needle attached helps prevent leaking, blocking of the needle, and air from entering the Pen.

Step 16:

- Replace the Pen cap by pushing it straight on (See Figure T).

After your injection:

- Put your used needles in a FDA-cleared sharps disposal container right away after use. Do not throw away (dispose of) loose needles in your household trash.
- If you do not have a FDA-cleared sharps disposal container, you may use a household container that is:
- made of a heavy-duty plastic
- can be closed with a tight-fitting, puncture-resistant lid, without sharps being able to come out
- upright and stable during use
- leak-resistant
- properly labeled to warn of hazardous waste inside the container
- When your sharps disposal container is almost full, you will need to follow your community guidelines for the right way to dispose of your sharps disposal container. There may be state or local laws about how you should throw away used needles and syringes. Do not reuse or share needles or syringes with another person. For more information about safe sharps disposal, and for specific information about sharps disposal in the state that you live in, go to the FDA’s website at: http://www.fda.gov/safesharpsdisposal.
- Do not dispose of your used sharps disposal container in your household trash unless your community guidelines permit this. Do not recycle your used sharps disposal container.

How should I store my FIASP FlexTouch Pen?

Before use:

- Store unused FIASP FlexTouch Pens in the refrigerator at 36°F to 46°F (2°C to 8°C) or at room temperature below 86°F (30°C).
- Do not freeze FIASP. Do not use FIASP if it has been frozen.
- Unused Pens may be used until the expiration date printed on the label, if kept in the refrigerator.
- If FIASP FlexTouch Pens are stored at room temperature prior to first use, it should be used or thrown away within 28 days.

Pen in use:

- Store the Pen you are currently using without the needle attached at room temperature below 86°F (30°C) or in the refrigerator at 36°F to 46°F (2°C to 8°C) for up to 28 days.
- Keep FIASP away from excessive heat or light.
- The FIASP FlexTouch Pen you are using is to be thrown away after 28 days, even if it still has insulin left in it and the expiration date has not passed.

General Information about the safe and effective use of FIASP:

- Keep FIASP FlexTouch Pens and needles out of the reach of children.
- Always use a new needle for each injection.
- Do not share FIASP FlexTouch Pens or needles with other people. You may give other people a serious infection, or get a serious infection from them.

This Instructions for Use has been approved by the U.S. Food and Drug Administration.

Manufactured by:

Novo Nordisk Inc.

800 Scudders Mill Road

Plainsboro, NJ 08536

1-800-727-6500

U.S. License No. 1261

Revised: 06/2023

For more information go to

www.FIASPflextouch.com

© 2023 Novo Nordisk

INSTRUCTIONS FOR USE

FIASP® [fee’asp] PenFill®

(insulin aspart)

injection, for subcutaneous use

3 mL cartridge: 100 units/mL (U-100)

- Do not share your PenFill cartridge or PenFill cartridge compatible insulin delivery device with other people, even if the needle has been changed. You may give other people a serious infection, or get a serious infection from them.
- Your healthcare provider should show you or your caregiver how to inject FIASP the right way before you inject it for the first time.
- FIASP PenFillcartridge 100 units/mL is a prefilled single-patient-use cartridge containing 300 units of U-100 FIASP (insulin aspart) injection.
- After you insert the PenFill cartridge in your device, you can use it for multiple injections. Read the instruction manual that comes with your insulin delivery device for complete instructions on how to use the PenFill cartridge with the device.
- This PenFill cartridge is not recommended for use by the blind or visually impaired without the assistance of a person trained in the proper use of the product and your insulin delivery device.
- If using a new FIASP PenFill cartridge, start with Step 1.
- If the FIASP PenFill cartridge has already been used, start with Step 2.

Supplies you will need to give your FIASP injection:

- FIASP PenFill cartridge
- Novo Nordisk 3 mL PenFill cartridge compatible insulin delivery device
- 1 new NovoFine®, NovoFine® Plus, or NovoTwist® needle
- Alcohol swab
- Adhesive bandage
- Cotton gauze
- A sharps container for throwing away used PenFill cartridges and needles. See “After your injection” at the end of these instructions.

(Figure A)

How to use the FIASP PenFill cartridge

- Wash your hands with soap and water.
- Before you start to prepare your injection, check the FIASP PenFill cartridge label to make sure that it contains the insulin you need. This is especially important if you take more than 1 type of insulin.
- The tamper-resistant foil should be in place before the first use. If the foil has been broken or removed before your first use of the cartridge, do not use it. Call Novo Nordisk at 1-800-727-6500.
- Carefully look at the cartridge and the insulin inside it. Check that the FIASP cartridge:
  - is not damaged, for example cracked or leaking
  - is not loose on the threaded end
- FIASP should look clear and colorless. Do not use FIASP if it is cloudy or colored or if the threaded end is loose (See Figure B).

(Figure B)

Step 1:

- Insert a 3 mL cartridge with the threaded end first into your Novo Nordisk 3 mL PenFill cartridge compatible insulin delivery device (See Figure C).
- If you drop your device, check the insulin cartridge for damage such as cracks or leaking. If your cartridge is damaged, throw it away and use a new one.

(Figure C)

Prepare your device with a new needle

Step 2:

- Take a new needle, and tear off the paper tab. Always use a new needle for each injection to make sure the needle is free of germs (sterile) and to prevent blocked needles. Do not attach a new needle to your device until you are ready to give your injection. Do not reuse or share your needles with other people. You may give others a serious infection, or get a serious infection from them.
- Be careful not to bend or damage the needle before you use it.
- Push the needle straight onto the device. Turn the needle clockwise until it is on tight (See Figure D).

(Figure D)

Step 3:

- Pull off the outer needle cap (See Figure E). Do not throw it away. You will need it after the injection to safely remove the needle.

(Figure E)

Step 4:

- Pull off the inner needle cap and throw it away (See Figure F). Do not try to put the inner needle cap back on the needle.

(Figure F)

A drop of insulin may appear at the needle tip. This is normal, but you must still check the insulin flow.

Check the insulin flow

Step 5:

- Small amounts of air may collect in the cartridge during normal use. You must do an airshot before each injection to avoid injecting air and to make sure you receive the prescribed dose of your medicine.
- Do the airshot as described in the instruction manual that comes with your device.
- Keep testing your Novo Nordisk 3 mL PenFill cartridge compatible insulin delivery device until you see insulin at the needle tip. If you still do not see a drop of insulin after 6 times, change the needle and repeat this step. This makes sure that any air bubbles are removed and that insulin is getting through the needle (See Figure G).

(Figure G)

Select your dose

Step 6:

- Check to make sure that the dose counter is set to 0.
- Turn the dose selector clockwise to select the dose you need to inject (See Figure H). The pointer should line up with your dose. When turning the dose selector, be careful not to press the dose button as insulin will come out. You will hear a click for every single unit dialed. Do not set the dose by counting the number of clicks you hear because you may get an incorrect dose.
- Refer to your insulin delivery device manual if necessary.

(Figure H)

Inject your dose

Step 7:

- Do the injection exactly as shown to you by your healthcare provider. Your healthcare provider should tell you if you need to pinch the skin before injecting.
- You should take your dose of FIASP at the start of a meal or within 20 minutes after starting a meal.
- FIASP can be injected under the skin (subcutaneously) of your stomach area (abdomen), upper legs (thighs), or upper arms (See Figure I).

(Figure I)

- Change (rotate) your injection sites within the area you choose for each dose to reduce your risk of getting lipodystrophy (pits in skin or thickened skin) and localized cutaneous amyloidosis (skin with lumps) at the injection sites. Do not use the same injection site for each injection. Do not inject where the skin has pits, is thickened, or has lumps. Do not inject where the skin is tender, bruised, scaly or hard, or into scars or damaged skin.
- Clean your injection site with an alcohol swab. Let your skin dry. Do not touch this area again before injecting.
- Insert the needle into your skin. Press and hold down the dose button until the dose counter shows “0”. Continue to keep the dose button pressed and keep the needle in your skin and slowly count to 6 (see Figure J).
- Remove the needle from your skin.

(Figure J)

You may see a drop of FIASP at the needle tip after injecting. This is normal and has no effect on the dose you just received. If blood appears after you take the needle out of your skin, press the injection site lightly with a cotton gauze and cover with an adhesive bandage, if necessary. Do not rub the area.

After your injection

Step 8:

- Lay your outer needle cap on a flat surface. Carefully, lead the needle tip into the outer needle cap without touching the needle (See Figure K) and push the outer needle cap completely on.

(Figure K)

- Hold the black cartridge holder on the insulin delivery device and unscrew the needle counterclockwise (See Figure L).

(Figure L)

- Throw away (dispose of) the needle in an FDA-cleared sharps container as your healthcare professional has instructed you.
- Put your empty FIASP PenFill cartridge and used needles in a FDA-cleared sharps disposal container right away after use. Do not throw away (dispose of) loose needles and PenFill cartridges in your household trash.
- If you do not have a FDA-cleared sharps disposal container, you may use a household container that is:
- made of a heavy-duty plastic
- can be closed with a tight-fitting, puncture-resistant lid, without sharps being able to come out
- upright and stable during use
- leak-resistant
- properly labeled to warn of hazardous waste inside the container
- When your sharps disposal container is almost full, you will need to follow your community guidelines for the right way to dispose of your sharps disposal container. There may be state or local laws about how you should throw away used needles and syringes. Do not reuse or share your needles or syringes with other people. For more information about the safe sharps disposal, and for specific information about sharps disposal in the state that you live in, go to the FDA’s website at: http://www.fda.gov/safesharpsdisposal.
- Do not dispose of your used sharps disposal container in your household trash unless your community guidelines permit this. Do not recycle your used sharps disposal container.

Step 9:

- Keep the 3 mL PenFill cartridge in the device. Do not store your device with a needle attached. This will prevent infection or leakage of insulin and will make sure that you receive the right dose of FIASP.
- Put the pen cap on your device after each use to protect the insulin from light (See Figure M).

(Figure M)

How should I store my FIASP PenFill cartridge?

Before use:

- Store unused FIASP PenFill cartridges in the refrigerator at 36°F to 46°F (2°C to 8°C).
- Do not freeze FIASP. Do not use FIASP if it has been frozen.
- Unused PenFill cartridges may be used until the expiration date printed on the label, if kept in the refrigerator.
- If FIASP is stored mistakenly outside of refrigeration between 47°F (9°C) to 86°F (30°C) prior to first use, it should be used within 28 days or thrown away.

PenFill cartridges in use:

- Store the PenFill cartridge you are currently using in the insulin delivery device at room temperature below 86°F (30°C) for up to 28 days. Do not refrigerate.
- Keep FIASP away from heat or light.
- The FIASP PenFill cartridge you are using should be thrown away after 28 days, even if it still has insulin left in it.

General Information about the safe and effective use of FIASP.

- Keep FIASP PenFill cartridges and needles out of the reach of children.
- Do not share FIASP PenFill cartridges or needles with other people. You may give other people a serious infection, or get a serious infection from them.
- Always carry extra insulin of the same type(s) you use in case of loss or damage.

This Instructions for Use has been approved by the U.S. Food and Drug Administration.

© 2023 Novo Nordisk

Manufactured by:

Novo Nordisk Inc.

800 Scudders Mill Road

Plainsboro, NJ 08536

1-800-727-6500

U.S. License No. 1261

Revised: 06/2023

INSTRUCTIONS FOR USE

FIASP® [fee’asp] PumpCart®

(insulin aspart)

injection, for subcutaneous use

1.6 mL cartridge: 100 units/mL (U-100)

- Please read the pump manual (user guide) that comes with your insulin pump.
- Only use FIASP PumpCart with a compatible insulin pump. Check the insulin pump manual for instructions to see if FIASP PumpCart can be used with the pump. Do not use with other devices that are not designed for use with FIASP PumpCart.
- FIASP PumpCart is ready for use directly in the pump. Using the wrong device may result in the wrong insulin dosing and lead to high blood sugar (hyperglycemia) or low blood sugar (hypoglycemia).
- Do not share your PumpCart cartridge with other people. You may give other people a serious infection or get a serious infection from them.
- Do not use the PumpCart cartridge if you are blind or visually impaired without the assistance of a person trained in the proper use of the PumpCart.
- Do not mix with any other insulins.
- Do not refill FIASP PumpCart. When it is empty, throw away (dispose) the cartridge.
- Do not use FIASP PumpCart in an insulin pen.

Preparing and Using the FIASP PumpCart cartridge

- Take FIASP PumpCart out of its package.
- Check the label to make sure that it is FIASP PumpCart and confirm that you are using a compatible insulin pump.
- Check the expiry date (EXP) – which is on the label and the carton.
- See picture A. Do not use the cartridge if any damage or leakage is seen, if the plunger has moved, or if the bottom of the plunger is visible above the white label band. This could be a result of leakage of insulin. Contact Novo Nordisk If you suspect that your FIASP PumpCart cartridge is damaged.
- Check that the insulin in FIASP PumpCart is clear and colorless. If the insulin looks cloudy, do not use FIASP PumpCart. The cartridge may contain small bubbles.
- Wash your hands with soap and water prior to installing the cartridge in your insulin pump.
- Follow the instructions in the pump user manual to insert a new FIASP PumpCart cartridge in your pump and to remove the FIASP PumpCart cartridge from your pump.
- Replace the FIASP PumpCart cartridge at least every 4 days, or according to the pump user manual, whichever is shorter, even if you have not used all of the insulin.
- Change the infusion sets and the infusion set insertion site according to the insulin pump manufacturers’ user manual.
- Throw away FIASP PumpCart in the pump reservoir if it has been exposed to temperatures higher than 98.6°F (37°C).
How should I dispose my FIASP PumpCart cartridge?
- Put your empty FIASP PumpCart in a FDA-cleared sharps disposal container right away after use. Do not throw away (dispose of) Fiasp PumpCart in your household trash.
- If you do not have a FDA-cleared sharps disposal container, you may use a household container that is:
  - made of a heavy-duty plastic
  - can be closed with a tight-fitting, puncture-resistant lid, without sharps being able to come out
  - upright and stable during use
  - leak-resistant
  - properly labeled to warn of hazardous waste inside the container
- When your sharps disposal container is almost full, you will need to follow your community guidelines for the right way to dispose of your sharps disposal container. There may be state or local laws about how you should throw away used needles and syringes. For more information about safe sharps disposal, and for specific information about sharps disposal in the state that you live in, go to the FDA’s website at: http://www.fda.gov/safesharpsdisposal. Do not dispose of your used sharps disposal container in your household trash unless your community guidelines permit this. Do not recycle your used sharps disposal container.

How should I store my FIASP PumpCart cartridge?

- Not in-use (unopened) cartridges: Refrigerate at 36°F to 46°F (2°C to 8°C) in the original carton until expiration or for up to 18 days below 86°F (30°C).
- In-use (opened) cartridge: Do not refrigerate. Keep below 98.6°F (37°C) for up to 4 days. The maximum time at room temperature is 18 days including 4 days in the pump.
- Do not freeze.
- Keep FIASP PumpCart cartridge away from heat or light.

General Information about the safe and effective use of FIASP PumpCart cartridge

- Keep FIASP PumpCart out of the reach of children.
- Always carry extra insulin of the same type you use in case of loss or damage.

This Instructions for Use has been approved by the U.S. Food and Drug Administration.

© 2023 Novo Nordisk

Manufactured by:

Novo Nordisk Inc.

800 Scudders Mill Road

Plainsboro, New Jersey 08536

US License Number 1261

Revised: 06/2023

PRINCIPAL DISPLAY PANEL - VIAL

NDC 0169-3201-11 List 320111

FIASP®

(insulin apart) injection

100 units/mL (U-100)

For subcutaneous or intravenous use

Rx only One 10 mL multi-dose vial

PRINCIPAL DISPLAY PANEL - FLEXTOUCH

NDC 0169-3204-15 List 320415

FIASP® FlexTouch®

(insulin aspart) injection

For Single-Patient Use Only

100 units/mL (U-100)

For subcutaneous use only

Rx Only

Recommended for use with NovoFine® or

NovoFine® Plus disposable needles.

Keep in a refrigerator at 36° to 46°F (2° to 8°C) until first use.

After first use store at 36° to 86°F (2° to 30°C) up to 28 days.

Do not freeze.

Protect from light.

Dispense in this sealed carton.

5×3 mL Prefilled Pens

PRINCIPAL DISPLAY PANEL - PenFill

NDC 0169-3205-15 List 320515

FIASP® PenFill®

(insulin aspart) injection

For Single-Patient Use Only

100 units/mL (U-100)

For Subcutaneous Use

For use with Novo Nordisk 3 mL PenFill® cartridge compatible delivery devices, NovoPen® Echo®, and NovoFine®/NovoFine® Plus disposable needles.

Not in-use (unopened) cartridges: Refrigerate at 36°F to 46°F (2°C to 8°C) in the original carton. In-use (opened) cartridge: Keep at room temperature below 86°F (30°C). Once stored at room temperature, discard after 28 days. Do not freeze. Protect from light.

Rx only

3 mL cartridges

5 cartridges per package

Principal Display Panel - PumpCart

NDC 0169-3206-15 List 320615

Fiasp® PumpCart®

(insulin aspart) injection

For Single-Patient Use Only

100 units/mL (U-100)

For use with a compatible insulin pump only

For Subcutaneous Use

Not in-use (unopened) cartridges: Refrigerate at 36°F to 46°F (2°C to 8°C) until expiration or for up to 18 days below 86°F (30°C) in the original carton.

In-use (opened) cartridges: Keep below 98.6°F (37°C) for up to 4 days.

Do not freeze. Protect from light.

Rx only

1.6 mL cartridges

5 cartridges per package